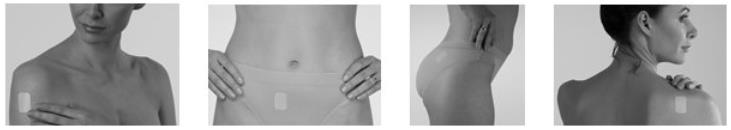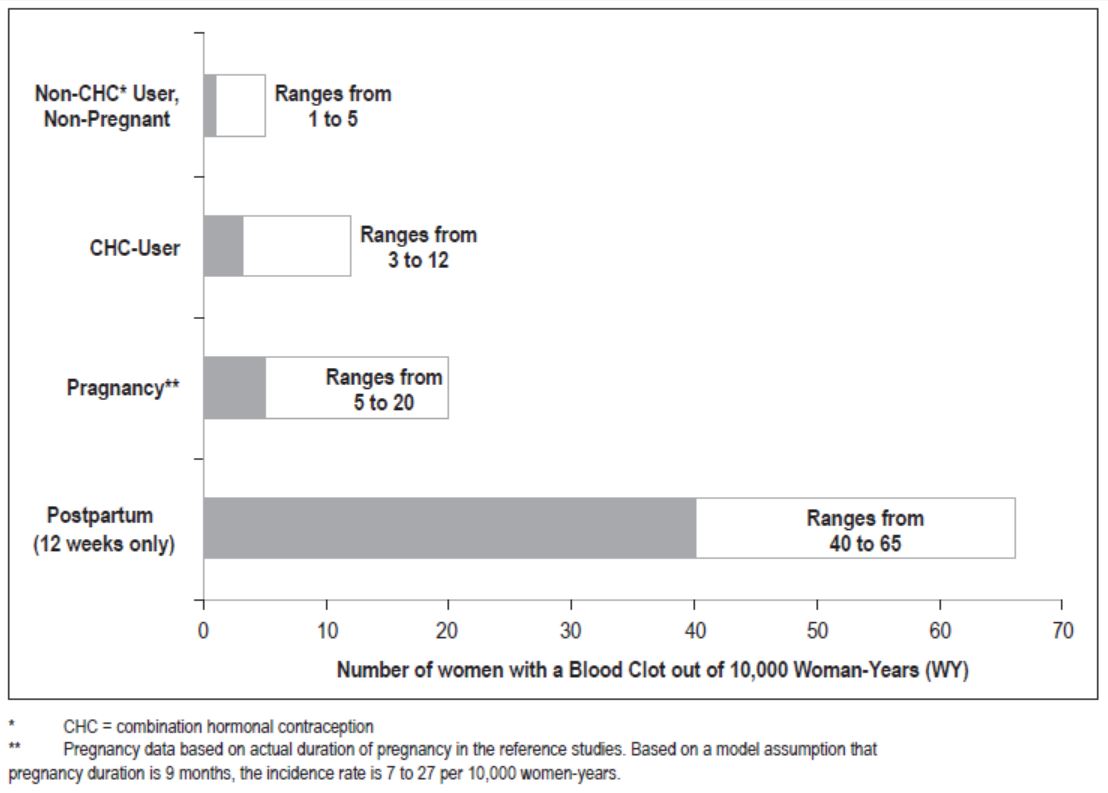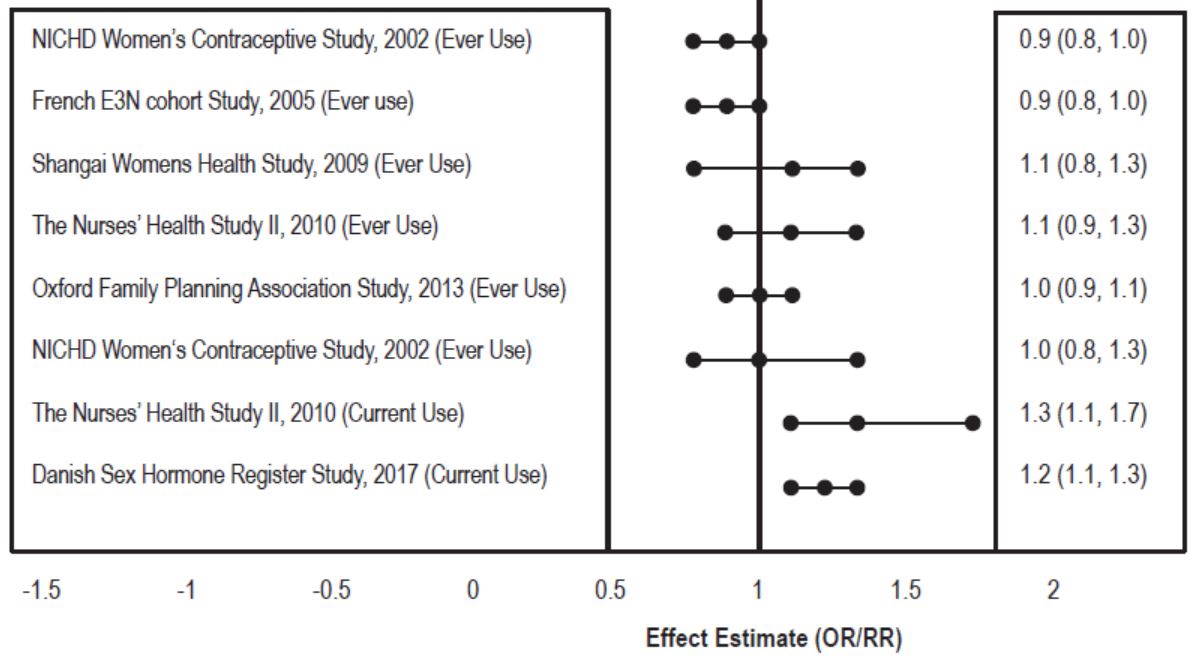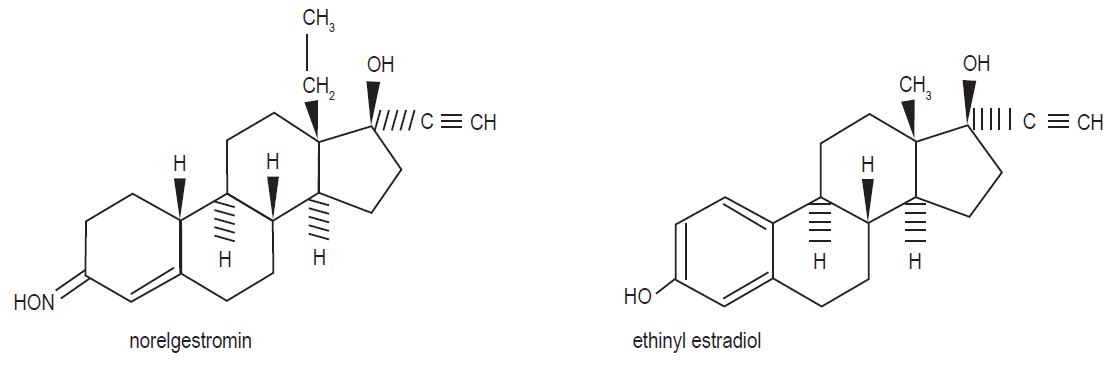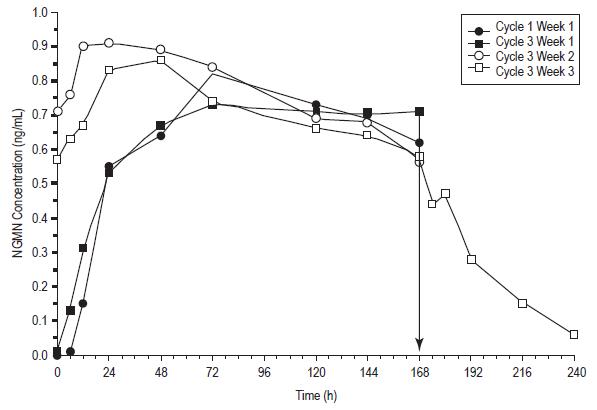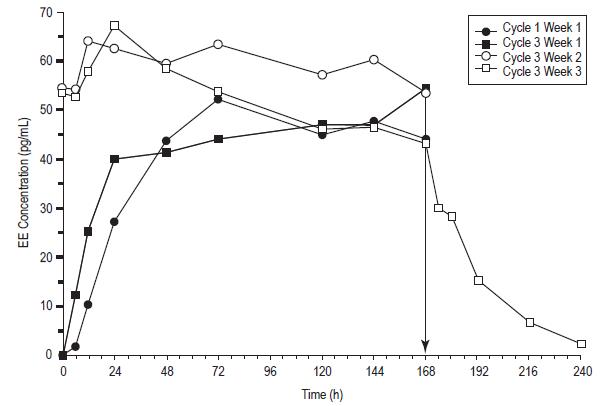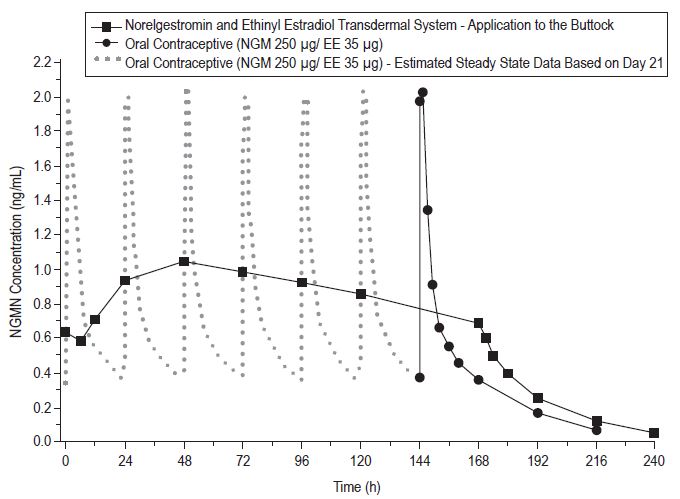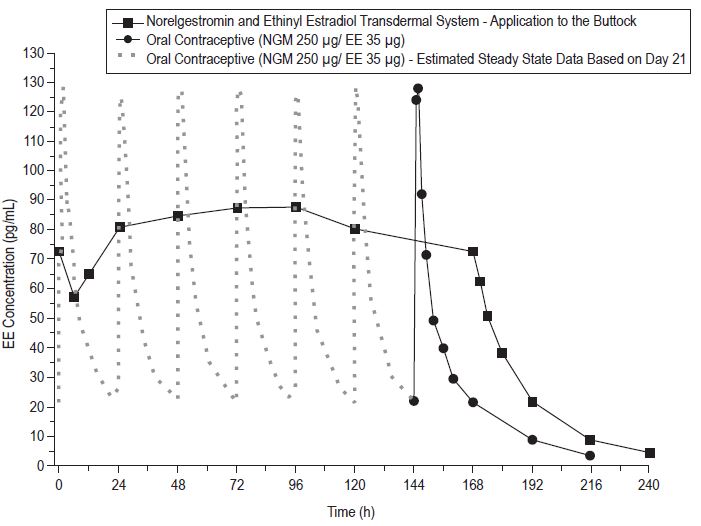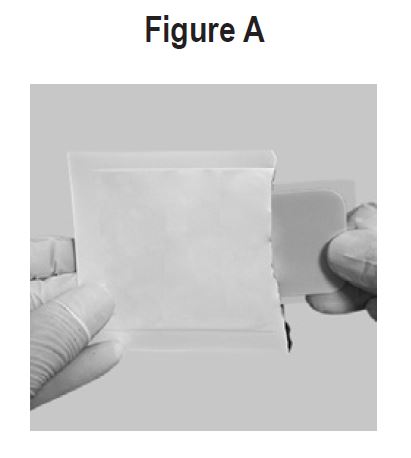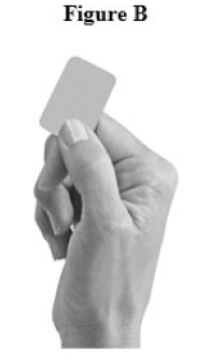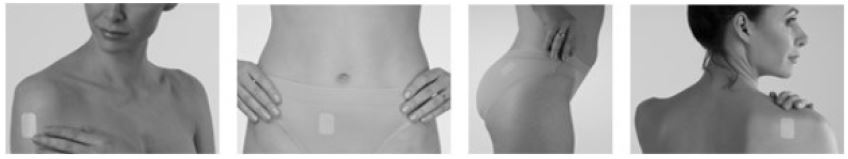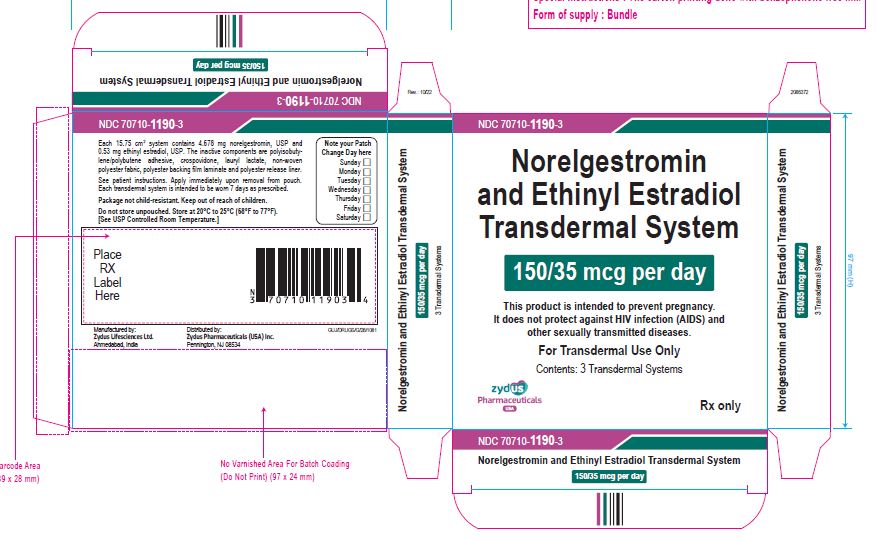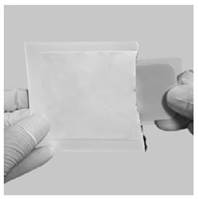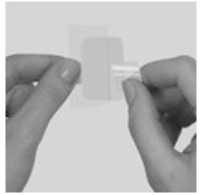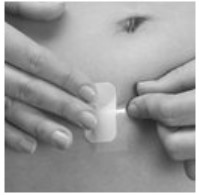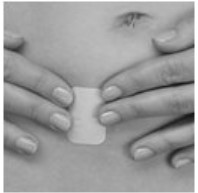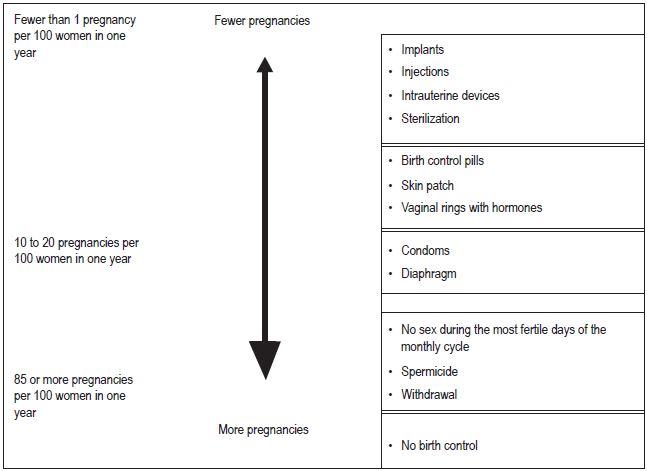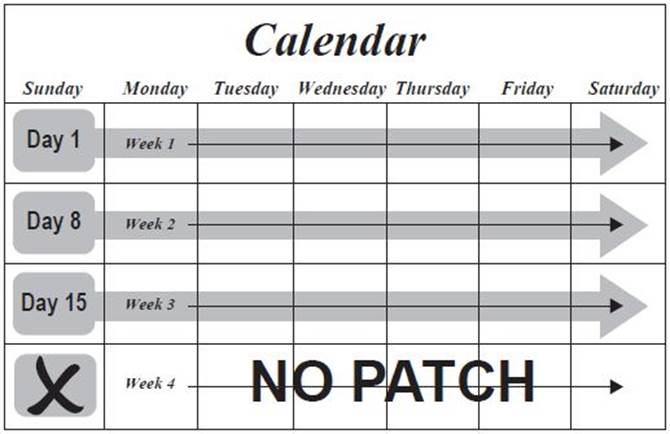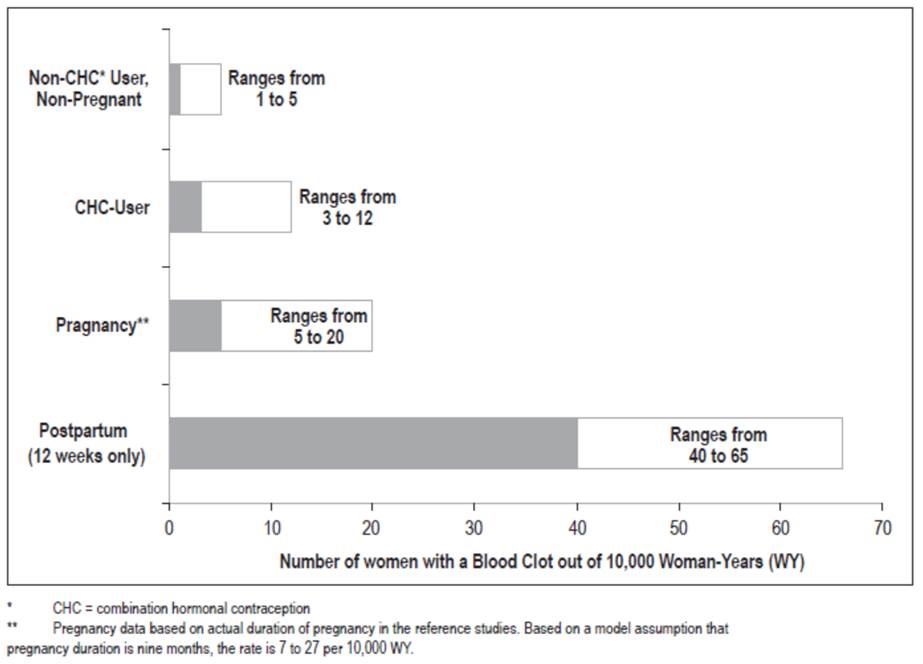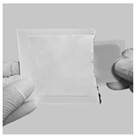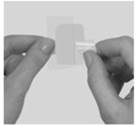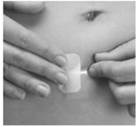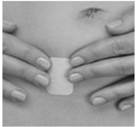 DRUG LABEL: norelgestromin and ethinyl estradiol
NDC: 70710-1190 | Form: PATCH
Manufacturer: Zydus Pharmaceuticals USA Inc.
Category: prescription | Type: HUMAN PRESCRIPTION DRUG LABEL
Date: 20241127

ACTIVE INGREDIENTS: NORELGESTROMIN 150 ug/1 mg; ETHINYL ESTRADIOL 35 ug/1 mg
INACTIVE INGREDIENTS: CROSPOVIDONE; LAURYL LACTATE

HIGHLIGHTS OF PRESCRIBING INFORMATION

These highlights do not include all the information needed to use NORELGESTROMIN AND ETHINYL ESTRADIOL TRANSDERMAL SYSTEM safely and effectively. See full prescribing information for NORELGESTROMIN AND ETHINYL ESTRADIOL TRANSDERMAL SYSTEM
NORELGESTROMIN AND ETHINYL ESTRADIOL transdermal system
Initial U.S. Approval: 2001

WARNING: CIGARETTE SMOKING AND SERIOUS CARDIOVASCULAR EVENTS and CONTRAINDICATED IN WOMEN WITH A BMI |GTE 30 kg/m2

WARNING: CIGARETTE SMOKING AND SERIOUS CARDIOVASCULAR EVENTS and CONTRAINDICATED IN WOMEN WITH A BMI ≥ 30 kg/m^2

See full prescribing information for complete boxed warning.

● Norelgestromin and ethinyl estradiol transdermal is contraindicated in women over 35 years old who smoke. Cigarette smoking increases the risk of serious cardiovascular events from combination hormonal contraceptive (CHC) use. (4, 5.1)

● Norelgestromin and ethinyl estradiol transdermal is contraindicated for use in women with a BMI ≥ 30 kg/m^2. Women with a BMI ≥ 30 kg/m^2who use norelgestromin and ethinyl estradiol transdermal may have a higher risk of venous thromboembolic events compared with women with a lower BMI. (4, 5.1, 8.8)

1 INDICATIONS AND USAGE

Norelgestromin and ethinyl estradiol transdermal system is an estrogen/progestin combination hormonal contraceptive (CHC), indicated for the prevention of pregnancy in women with a BMI < 30 kg/m^2 for whom combined hormonal contraceptive is appropriate. (1)

Limitations of Use:

Norelgestromin and ethinyl estradiol transdermal system may be less effective in preventing pregnancy in women at or above 198 lbs (90 kg). (1, 4, 14)

2 DOSAGE AND ADMINISTRATION

- Norelgestromin and ethinyl estradiol transdermal system uses a 28-day (4-week) cycle. Apply a new patch to the upper outer arm, abdomen, buttock or back each week for 3 weeks (21 total days). Week 4 is patch-free. (2.1,2.3)
- Apply each new patch on the same day of the week. Wear only one patch at a time. (2.1)
- Do not cut or alter the patch in any way. (2.1)

3 DOSAGE FORMS AND STRENGTHS

Transdermal system: 150 mcg/day norelgestromin and 35 mcg/day ethinyl estradiol. (3)

4 CONTRAINDICATIONS

- At high risk of arterial or venous thromboembolic events (4)
- BMI ≥ 30 kg/m^2(4)
- Breast cancer or other estrogen- or progestin-sensitive cancer (4)
- Liver tumors or liver disease (4)
- Undiagnosed abnormal uterine bleeding (4)
- Pregnancy (4)
- Co-administration with Hepatitis C drug combinations containing ombitasvir/paritaprevir/ritonavir, with or without dasabuvir (4)

5 WARNINGS AND PRECAUTIONS

- Vascular risks : Stop norelgestromin and ethinyl estradiol transdermal system if a thrombotic event occurs. Stop at least 4 weeks before and through 2 weeks after major surgery.

Start no earlier than 4 weeks after delivery, in women who are not breastfeeding. Consider cardiovascular risk factors before initiating in all women, particularly those over 35 years. (5.1)

- Liver disease : Discontinue norelgestromin and ethinyl estradiol transdermal system if jaundice occurs. (5.3)
- High blood pressure : Do not prescribe norelgestromin and ethinyl estradiol transdermal system for women with uncontrolled hypertension or hypertension with vascular disease. (5.5)
- Carbohydrate and lipid metabolic effects : Monitor prediabetic and diabetic women taking norelgestromin and ethinyl estradiol transdermal system. Consider an alternate contraceptive method for women with uncontrolled dyslipidemia. (5.7)
- Headache : Evaluate significant change in headaches and discontinue norelgestromin and ethinyl estradiol transdermal system if indicated. (5.8)
- Uterine bleeding : Evaluate irregular bleeding or amenorrhea. (5.9)

6 ADVERSE REACTIONS

The most frequent adverse reactions reported during clinical trials (≥ 5%) were breast symptoms, nausea/vomiting, headache, application site disorder, abdominal pain, dysmenorrhea, vaginal bleeding and menstrual disorders, and mood, affect and anxiety disorders. (6.1)

To report SUSPECTED ADVERSE REACTIONS, contact Zydus Pharmaceuticals (USA) Inc. at 1-877-993-8779 or FDA at 1-800-FDA-1088 or www.fda.gov/medwatch.

7 DRUG INTERACTIONS

Drugs or herbal products that induce certain enzymes (for example CYP3A4) may decrease the effectiveness of CHCs or increase breakthrough bleeding. Counsel patients to use a back-up or alternative method of contraception when enzyme inducers are used with CHCs. (7.1)

8 USE IN SPECIFIC POPULATIONS

Nursing mothers: Not recommended; can decrease milk production. (8.3)

FULL PRESCRIBING INFORMATION

WARNING: CIGARETTE SMOKING AND SERIOUS CARDIOVASCULAR EVENTS and CONTRAINDICATED IN WOMEN WITH A BMI |GTE 30 kg/m2

• Cigarette Smoking and Serious Cardiovascular Events

Cigarette smoking increases the risk of serious cardiovascular events from hormonal contraceptive use. This risk increases with age, particularly in women over 35 years of age, and with the number of cigarettes smoked. For this reason, CHCs, including norelgestromin and ethinyl estradiol transdermal system, are contraindicated in women who are over 35 years of age and smoke [see Contraindications (4) and Warnings and Precautions (5.1)].

• Contraindicated in Women with a BMI ≥ 30 kg/m^2

Norelgestromin and ethinyl estradiol transdermal system is contraindicated in women with a BMI ≥ 30 kg/m^2. The risk of VTE may be greater with norelgestromin and ethinyl estradiol transdermal in women with a BMI ≥ 30 kg/m^2 compared to women with a lower BMI [see Contraindications (4) and Warnings and Precautions (5.1)].

1 INDICATIONS AND USAGE

Norelgestromin and ethinyl estradiol transdermal system is indicated for the prevention of pregnancy in women with a body mass index (BMI) < 30 kg/m^2 for whom a combined hormonal contraceptive is appropriate.

Limitations of Use:

Norelgestromin and ethinyl estradiol transdermal system may be less effective in preventing pregnancy in women who weigh 198 lbs (90 kg) or more. Norelgestromin and ethinyl estradiol transdermal system is contraindicated for use in women with BMI ≥ 30 kg/m2 [see Contraindications (4), Warnings and Precautions (5.1) and Clinical Studies (14)].

2 DOSAGE AND ADMINISTRATION

To achieve maximum contraceptive effectiveness, norelgestromin and ethinyl estradiol transdermal system must be used exactly as directed.

Complete instructions to facilitate patient counseling on proper system usage may be found in the FDA-Approved Patient Labeling.

2.1 How to Use Norelgestromin and Ethinyl Estradiol Transdermal System

The norelgestromin and ethinyl estradiol transdermal system uses a 28-day (4-week) cycle. A new patch is applied each week for 3 weeks (21 total days). Week 4 is patch-free. Withdrawal bleeding is expected during this time.

Every new patch should be applied on the same day of the week. This day is known as the "Patch Change Day." For example, if the first patch is applied on a Monday, all subsequent patches should be applied on a Monday. Only one patch should be worn at a time.

Do not cut, damage or alter the norelgestromin and ethinyl estradiol transdermal system patch in any way. If the norelgestromin and ethinyl estradiol transdermal system patch is cut, damaged or altered in size, contraceptive efficacy may be impaired.

On the day after Week 4 ends, a new 4-week cycle is started by applying a new patch. Under no circumstances should there be more than a 7-day patch-free interval between dosing cycles.

2.2 How to Start Using Norelgestromin and Ethinyl Estradiol Transdermal System

There are multiple options for starting the Norelgestromin and Ethinyl Estradiol transdermal system, and the woman should choose the option that is most appropriate (see Table 1):

Table 1: Instructions for Administration

Starting Norelgestromin and Ethinyl Estradiol Transdermal System in women with no current use of hormonal contraception
The woman has two options for starting the patch and she should choose the option that is right for her:
First Day Start
- The woman should apply her first patch during the first 24 hours of her menstrual period. If a patch is applied after the first 24 hours of menstruation, non-hormonal back-up contraception (such as condoms and spermicide, or diaphragm and spermicide) is needed for the first 7 days of the first cycle only.
- The woman should apply a new patch each week for three weeks (21 total days). Every new patch should be applied on the same day of the week. This day is known as the "Patch Change Day." For example, if the first patch is applied on a Monday, all subsequent patches should be applied on a Monday. Only one patch should be worn at a time.
- No patch is worn during Week Four (the "Patch-Free Week"). Withdrawal bleeding is expected during this time.
- On the day after Week 4 ends, a new 4-week cycle is started by applying a new patch. Under no circumstances should there be more than a 7-day patch-free interval between dosing cycles.
Sunday Start
- The woman should apply her first patch on the first Sunday after her menstrual period begins.
- With this option, a non-hormonal backup method of birth control, such as a condom and spermicide or diaphragm and spermicide, is needed for the first 7 days of the first cycle only.
- If her period starts on a Sunday, the first patch should be applied that day, and no backup contraception is needed.
Switching from another contraceptive method
Oral combination hormonal contraception (oral CHC) | • If the woman is switching from the pill to Norelgestromin and Ethinyl Estradiol Transdermal System, she should complete her current pill cycle and apply the first Norelgestromin and Ethinyl Estradiol Transdermal System patch on the day she would normally start her next pill • If she does not get her period within a week after taking the last active pill, she should check with her healthcare professional to be sure that she is not pregnant, but she may go ahead and start Norelgestromin and Ethinyl Estradiol Transdermal System for contraception. • If the patch is applied more than a week after taking the last active pill, she should use a non-hormonal back-up contraception (such as condoms and spermicide, or diaphragm and spermicide) concurrently for the first 7 days of patch use.
Transdermal system | • If the woman is switching from another contraceptive transdermal system to Norelgestromin and Ethinyl Estradiol Transdermal System, she should complete the current transdermal system cycle and apply the first Norelgestromin and Ethinyl Estradiol Transdermal System patch on the day the next transdermal system cycle would normally start. • If she does not get her period within a week after removing the last transdermal system, she should check with her healthcare professional to be sure that she is not pregnant, but she may go ahead and start Norelgestromin and Ethinyl Estradiol Transdermal System for contraception. If Norelgestromin and Ethinyl Estradiol Transdermal System is applied more than a week after removal of the last patch, nonhormonal back-up contraception (such as condoms and spermicide, or diaphragm and spermicide) should be used concurrently for the first 7 days of patch use.
Vaginal ring | • If the woman is switching from the vaginal ring to Norelgestromin and Ethinyl Estradiol Transdermal System, she should complete her current vaginal ring cycle and apply the first Norelgestromin and Ethinyl Estradiol Transdermal System patch on the day she would normally insert her next vaginal ring. • If she does not get her period within a week after removing the last vaginal ring, she should check with her healthcare professional to be sure that she is not pregnant, but she may go ahead and start Norelgestromin and Ethinyl Estradiol Transdermal System for contraception. • If the patch is applied more than a week after removal of the last vaginal ring, she should use a non-hormonal back-up contraception (such as condoms and spermicide, or diaphragm and spermicide) concurrently for the first 7 days of patch use.
Injection | • If the woman is switching from an injection contraceptive to Norelgestromin and Ethinyl Estradiol Transdermal System, she should apply the first Norelgestromin and Ethinyl Estradiol Transdermal System patch on the day the next injection would normally occur.
Intrauterine system (IUS) | • If the woman is switching from an intrauterine system to Norelgestromin and Ethinyl Estradiol Transdermal System, she should apply the first Norelgestromin and Ethinyl Estradiol Transdermal System patch on the day of IUS removal. If the IUS is not removed on the first day of the menstrual cycle, nonhormonal backup contraception (such as condoms and spermicide, or diaphragm and spermicide) should be used concurrently for the first 7 days of patch use.
Implant | • If the woman is switching from an implant to Norelgestromin and Ethinyl Estradiol Transdermal System, she should apply the first Norelgestromin and Ethinyl Estradiol Transdermal System patch on the day of implant removal.
Progestin-only pill | • If the woman is switching from a progestin-only pill to Norelgestromin and Ethinyl Estradiol Transdermal System, she should apply the first Norelgestromin and Ethinyl Estradiol Transdermal System patch on the day the next progestin-only pill cycle would normally start.

Use after Childbirth

Start contraceptive therapy with norelgestromin and ethinyl estradiol transdermal system in women who elect not to breastfeed no sooner than 4 weeks after childbirth due to increased risk of thromboembolism. If a woman begins using norelgestromin and ethinyl estradiol transdermal system postpartum, and has not yet had a period, consider the possibility of ovulation and conception occurring prior to use of norelgestromin and ethinyl estradiol transdermal system, and instruct her to use an additional method of contraception, such as a condom and spermicide or diaphragm and spermicide, for the first 7 days. [See Warnings and Precautions (5.1) and Pregnancy (8.1).]

Use after Abortion or Miscarriage

After an abortion or miscarriage that occurs in the first trimester, norelgestromin and ethinyl estradiol transdermal system may be started immediately. An additional method of contraception is not needed if norelgestromin and ethinyl estradiol transdermal system is started immediately. If use of norelgestromin and ethinyl estradiol transdermal system is not started within 5 days following a first trimester abortion, the woman should follow the instructions for a woman starting norelgestromin and ethinyl estradiol transdermal system for the first time. In the meantime she should be advised to use a non-hormonal contraceptive method. Ovulation may occur within 10 days of an abortion or miscarriage.

Start norelgestromin and ethinyl estradiol transdermal system no earlier than 4 weeks after a second trimester abortion or miscarriage, due to the increased risk of thromboembolic disease. [See Contraindications (4) and Warnings and Precautions (5.1).]

2.3 How to Apply Norelgestromin and Ethinyl Estradiol Transdermal System

CHOOSING A PLACE ON THE BODY TO PUT THE PATCH

- The patch may be placed on the upper outer arm, abdomen, buttock or back in a place where it won't be rubbed by tight clothing. For example, it should not be placed under the waistband of clothing.
- The patch should not be placed on the breasts, on cut or irritated skin, or on the same location as the previous patch.

Before applying the patch:

- The woman should make sure the skin is clean and dry.
- She should not use lotions, creams, oils, powders, or make-up at the patch site. It may cause the patch to fail to stick properly or to become loose.

HOW TO APPLY THE PATCH

• The woman should tear open the pouch at the edge. She should gently remove the contents of the foil pouch and discard the additional piece of film above the patch.

• The woman should peel away half of the clear plastic. She should avoid touching the sticky surface with her fingers.

• The woman should apply the sticky side of the patch on the skin she has cleaned and dried. She should then remove the other half of the clear plastic and attach the entire patch to her skin.

• The woman should press firmly on the patch with the palm of her hand for 10 seconds, making sure that the whole patch adheres to her skin.
• She should run her fingers over the entire surface area to smooth out any "wrinkles" around the outer edges of the patch.

- The woman should check her patch every day to make sure all edges are sticking correctly.

WHEN TO CHANGE THE NORELGESTROMIN AND ETHINYL ESTRADIOL TRANSDERMAL SYSTEM PATCH

- The patch works for 7 days (1 week). The woman should apply a new patch on the same day each week (her Patch Change Day) for 3 weeks in a row. She must make sure she has removed her old patch prior to applying the new patch.
- During Week 4, she DOES NOT wear a patch. She must make sure she removes her old patch. (Her period should begin during this week.)
- Following Week 4, she repeats the cycle of three weekly applications followed by a patch-free week.

WHAT IF THE PATCH BECOMES LOOSE OR FALLS OFF?

The patch must stick securely to the skin to work properly. If the norelgestromin and ethinyl estradiol transdermal system patch becomes partially or completely detached and remains detached, insufficient drug delivery occurs. The woman should not try to reapply a patch if it is no longer sticky, if it has become stuck to itself or another surface, or if it has other material stuck to it.

If a patch edge lifts up:

- The woman should press down firmly on the patch with the palm of her hand for 10 seconds, making sure that the whole patch adheres to her skin. She should run her fingers over the entire surface area to smooth out any "wrinkles" around the edges of the patch.
- If her patch does not stick completely, she should remove it and apply a replacement patch.
- She should not tape or wrap the patch to her skin or reapply a patch that is partially adhered to clothing.

If the patch has been off or partially off:

- For less than 1 Day , she should try to reapply it. If the patch does not adhere completely, she should apply a new patch immediately. (No backup contraception is needed and her Patch Change Day will stay the same).
- For more than 1 Day or if she is not sure for how long , she may not be protected from pregnancy. To reduce this risk, she should apply a new patch and start a new 4-week cycle. She will now have a new Patch Change Day and MUST USE NON-HORMONAL BACKUP CONTRACEPTION (such as a condom and spermicide or diaphragm and spermicide) for the first week of her new cycle.

IF THE WOMAN FORGETS TO CHANGE HER PATCH

● at the start of any patch cycle (Week 1/Day 1): SHE MAY NOT BE PROTECTED FROM PREGNANCY. She should apply the first patch of her new cycle as soon as she remembers. There is now a new "Patch Change Day" and a new "Day 1." The woman must use back-up contraception, such as a condom and spermicide or diaphragm and spermicide, for the first week of the new cycle.

● in the middle of the patch cycle (Week 2/Day 8 or Week 3/Day 15),

○ for 1 or 2 days (up to 48 hours), she should apply a new patch immediately. The next patch should be applied on the usual "Patch Change Day." No back-up contraception is needed.

○ for more than 2 days (48 hours or more), SHE MAY NOT BE PROTECTED FROM PREGNANCY. She should stop the current contraceptive cycle and start a new 4-week cycle immediately by putting on a new patch. There is now a new "Patch Change Day" and a new "Day 1." The woman must use back-up contraception for 1 week.

● at the end of the patch cycle (Week 4/Day 22),

○ If the woman forgets to remove her patch, she should take it off as soon as she remembers. The next cycle should be started on the usual "Patch Change Day," which is the day after Day 28. No back-up contraception is needed.

Under no circumstances should there be more than a 7-day patch-free interval between cycles. If there are more than 7 patch-free days, THE WOMAN MAY NOT BE PROTECTED FROM PREGNANCY and back-up contraception, such as a condom and spermicide or diaphragm and spermicide, must be used for 7 days. As with combined oral contraceptives, the risk of ovulation increases with each day beyond the recommended drug-free period. If she has had intercourse during such an extended patch-free interval, consider the possibility of pregnancy.

Change Day Adjustment

If the woman wishes to change her Patch Change Day, she should complete her current cycle, removing the third norelgestromin and ethinyl estradiol transdermal system patch on the correct day. During the patch-free week, she may select an earlier Patch Day Change by applying a new norelgestromin and ethinyl estradiol transdermal system patch on the desired day. In no case should there be more than 7 consecutive patch-free days.

Breakthrough Bleeding or Spotting

In the event of unscheduled or breakthrough bleeding or spotting (bleeding that occurs on the days that norelgestromin and ethinyl estradiol transdermal system is worn), treatment should be continued. If unscheduled bleeding persists longer than a few cycles, consider causes other than norelgestromin and ethinyl estradiol transdermal system.

If the woman does not have scheduled or withdrawal bleeding (bleeding that should occur during the patch-free week), she should resume treatment on the next scheduled Change Day. If norelgestromin and ethinyl estradiol transdermal system has been used correctly, the absence of withdrawal bleeding is not necessarily an indication of pregnancy. Nevertheless, consider the possibility of pregnancy, especially if absence of withdrawal bleeding occurs in 2 consecutive cycles. Discontinue norelgestromin and ethinyl estradiol transdermal system if pregnancy is confirmed.

In Case of Skin Irritation

If patch use results in uncomfortable irritation, the patch may be removed and a new patch may be applied to a different location until the next Change Day. Only one patch should be worn at a time.

Additional Instructions for Dosing

Unscheduled bleeding, spotting, and amenorrhea are frequent reasons for patients discontinuing hormonal contraceptives. In case of breakthrough bleeding, as in all cases of irregular bleeding from the vagina, consider nonfunctional causes. In case of undiagnosed persistent or recurrent abnormal bleeding from the vagina, take adequate diagnostic measures to rule out pregnancy or malignancy. If pathology has been excluded, time or a change to another method of contraception may solve the problem.

Use of Hormonal Contraceptives in the Event of a Missed Menstrual Period

1. If the woman has not adhered to the prescribed schedule, consider the possibility of pregnancy at the time of the first missed period. Discontinue use of norelgestromin and ethinyl estradiol transdermal system if pregnancy is confirmed.
2. If the woman has adhered to the prescribed regimen and misses one period, she should continue using her contraceptive patches. However, if she has adhered to the prescribed regimen, misses one period and has symptoms associated with pregnancy, rule out pregnancy. Discontinue norelgestromin and ethinyl estradiol transdermal system use if pregnancy is confirmed.
3. If the woman has adhered to the prescribed regimen and misses two consecutive periods, rule out pregnancy. Discontinue norelgestromin and ethinyl estradiol transdermal system use if pregnancy is confirmed.

3 DOSAGE FORMS AND STRENGTHS

Norelgestromin and ethinyl estradiol transdermal system is available in one strength of 150 mcg/day norelgestromin (NGMN) and 35 mcg/day ethinyl estradiol (EE).

Norelgestromin and ethinyl estradiol transdermal system is a 15.75 cm^2 tan, transdermal system printed with "Norelgestromin and ethinyl estradiol 150/35 mcg per day" in red ink. Each system contains 4.678 mg norelgestromin, USP and 0.53 mg ethinyl estradiol, USP.

4 CONTRAINDICATIONS

Norelgestromin and ethinyl estradiol transdermal system is contraindicated in females who are known to have or develop the following conditions:

● At high risk of arterial or venous thromboembolic events. Examples include women who:

○ Smoke, if over age 35 [see Boxed Warning, and Warnings and Precautions (5.1)]

○ Have deep vein thrombosis or pulmonary embolism, now or in the past [see Warnings and Precautions (5.1)]

○ Have inherited or acquired hypercoagulopathies [see Warnings and Precautions (5.1)]

○ Have cerebrovascular disease [see Warnings and Precautions (5.1)]

○ Have coronary artery disease [see Warnings and Precautions (5.1)]

○ Have thrombogenic valvular or thrombogenic rhythm diseases of the heart (for example, subacute bacterial endocarditis with valvular disease, or atrial fibrillation) [see Warnings and Precautions (5.1)]

○ Have uncontrolled hypertension [see Warnings and Precautions (5.5)]

○ Have diabetes mellitus with vascular disease [see Warnings and Precautions (5.7)]

○ Have headaches with focal neurological symptoms or have migraine headaches with aura

■ Women over age 35 with any migraine headaches [see Warnings and Precautions (5.8)]

● Body Mass Index ≥ 30 kg/m^2 [see Warnings and Precautions (5.1)]

● Liver tumors, benign or malignant, or liver disease [see Warnings and Precautions (5.3), Use in Specific Populations (8.6) and Clinical Pharmacology (12.3)]

● Undiagnosed abnormal uterine bleeding [see Warnings and Precautions (5.9)]

● Pregnancy, because there is no reason to use hormonal contraceptives during pregnancy [see Warnings and Precautions (5.10) and Use in Specific Populations (8.1)]

● Current diagnosis of, or history of, breast cancer, which may be hormone-sensitive [see Warnings and Precautions (5.12)]

● Use of Hepatitis C drug combinations containing ombitasvir/paritaprevir/ritonavir, with or without dasabuvir, due to the potential for alanine aminotransferase (ALT) elevations [see Warnings and Precautions (5.4)]

5 WARNINGS AND PRECAUTIONS

5.1 Thromboembolic Disorders and Other Vascular Conditions

- Stop norelgestromin and ethinyl estradiol transdermal system if an arterial or venous thromboembolic event (VTE) occurs.
- Stop norelgestromin and ethinyl estradiol transdermal system if there is unexplained loss of vision, proptosis, diplopia, papilledema, or retinal vascular lesions. Evaluate for retinal vein thrombosis immediately.
- If feasible, stop norelgestromin and ethinyl estradiol transdermal system at least 4 weeks before and through 2 weeks after major surgery or other surgeries known to have an elevated risk of VTE. Discontinue use of norelgestromin and ethinyl estradiol transdermal system during prolonged immobilization and resume treatment based on clinical judgment.
- Start norelgestromin and ethinyl estradiol transdermal system no earlier than 4 weeks after delivery, in women who are not breastfeeding. The risk of postpartum VTE decreases after the third postpartum week, whereas the risk of ovulation increases after the third postpartum week.
- Before starting norelgestromin and ethinyl estradiol transdermal system, evaluate any past medical history or family history of thrombotic or thromboembolic disorders and consider whether the history suggests an inherited or acquired hypercoagulopathy [see Contraindications (4)].

Arterial Events

The use of CHCs increases the risk of cardiovascular events and cerebrovascular events, such as myocardial infarction and stroke. The risk is greater among older women (> 35 years of age), smokers, and women with hypertension, dyslipidemia, diabetes, or obesity. Norelgestromin and ethinyl estradiol transdermal system is contraindicated in women over 35 years of age who smoke [see Contraindications (4)]. Cigarette smoking increases the risk of serious cardiovascular events from CHC use. This risk increases with age, particularly in women over 35 years of age, and with the number of cigarettes smoked.

Venous Events

The use of CHCs increases the risk of venous thromboembolic events (VTEs), such as deep vein thrombosis and pulmonary embolism. Risk factors for VTEs include smoking, obesity, and family history of VTE, in addition to other factors that contraindicate use of CHCs. The risk of VTE may be greater with norelgestromin and ethinyl estradiol transdermal system in women with a BMI ≥ 30 kg/m^2 compared to women with a lower BMI [see Contraindications (4)].

While the increased risk of VTE associated with use of CHCs is well-established, the rates of VTE are even greater during pregnancy, and especially during the postpartum period (see Figure 1). The frequency of VTE in women using CHCs has been estimated to be 3 to 12 cases per 10,000 woman-years.

The risk of VTE is highest during the first year of use of CHCs and when restarting hormonal contraception after a break of 4 weeks or longer. This initial higher risk declines during the first year, but users of CHCs remain at an increased risk of VTE compared to non-users of CHCs. Based on results from a few studies, there is some evidence that this is true for non-oral products as well. The risk of thromboembolic disease due to CHCs gradually disappears after CHC use is discontinued.

Figure 1 shows the risk of developing a VTE for women who are not pregnant and do not use CHCs, for women who use CHCs with a range of doses and routes of administration, for pregnant women, and for women in the postpartum period. To put the risk of developing a VTE into perspective: If 10,000 women who are not pregnant and do not use CHCs are followed for one year, between 1 and 5 of these women will develop a VTE.

Figure 1

Likelihood of Developing a VTE Within One Year Among Pregnant and Non-Pregnant Women

5.2 Ethinyl Estradiol Exposure

Higher estrogen exposure may increase the risk of adverse reactions, including venous thromboembolism (VTE). The Area Under the Curve (AUC) for ethinyl estradiol (EE) is approximately 60% higher in women using norelgestromin and ethinyl estradiol transdermal system compared to oral contraceptives containing EE 35 mcg. In contrast, the peak concentration (Cmax) for EE is approximately 25% lower in women using norelgestromin and ethinyl estradiol transdermal system [see Clinical Pharmacology (12.3)].

5.3 Liver Disease

Impaired Liver Function

Do not use norelgestromin and ethinyl estradiol transdermal system in women with liver disease, such as acute viral hepatitis or severe (decompensated) cirrhosis of liver [see Contraindications (4)]. Discontinue norelgestromin and ethinyl estradiol transdermal system if jaundice develops. Acute or chronic disturbances of liver function may necessitate the discontinuation of CHC use until markers of liver function return to normal and CHC causation has been excluded.

Liver Tumors

Norelgestromin and ethinyl estradiol transdermal system is contraindicated in women with benign and malignant liver tumors [see Contraindications (4)]. Hepatic adenomas are associated with CHC use. An estimate of the attributable risk is 3.3 cases/100,000 CHC users. Rupture of hepatic adenomas may cause death through intra-abdominal hemorrhage.

Studies have shown an increased risk of developing hepatocellular carcinoma in long-term (> 8 years) CHC users. However, the risk of liver cancers in CHC users is less than one case per million users.

5.4 Risk of Liver Enzyme Elevations with Concomitant Hepatitis C Treatment

During clinical trials with the Hepatitis C combination drug regimen that contains ombitasvir/paritaprevir/ritonavir, with or without dasabuvir, ALT elevations greater than 5 times the upper limit of normal (ULN), including some cases greater than 20 times the ULN, were significantly more frequent in women using ethinyl estradiol-containing medications, such as CHCs. Discontinue norelgestromin and ethinyl estradiol transdermal system prior to starting therapy with the combination drug regimen ombitasvir/paritaprevir/ritonavir, with or without dasabuvir [see Contraindications (4)]. Norelgestromin and ethinyl estradiol transdermal system can be restarted approximately 2 weeks following completion of treatment with the Hepatitis C combination drug regimen.

5.5 High Blood Pressure

Norelgestromin and ethinyl estradiol transdermal system is contraindicated in women with uncontrolled hypertension or hypertension with vascular disease [see Contraindications (4)]. For women with well-controlled hypertension, monitor blood pressure and stop norelgestromin and ethinyl estradiol transdermal system if blood pressure rises significantly.

An increase in blood pressure has been reported in women taking hormonal contraceptives, and this increase is more likely in older women with extended duration of use. The incidence of hypertension increases with increasing concentrations of progestin.

5.6 Gallbladder Disease

Studies suggest a small increased relative risk of developing gallbladder disease among CHC users. Use of CHCs may also worsen existing gallbladder disease. A past history of CHC-related cholestasis predicts an increased risk with subsequent CHC use. Women with a history of pregnancy-related cholestasis may be at an increased risk for CHC-related cholestasis.

5.7 Carbohydrate and Lipid Metabolic Effects

Carefully monitor prediabetic and diabetic women who take norelgestromin and ethinyl estradiol transdermal system. CHCs may decrease glucose tolerance in a dose-related fashion. In a 6-cycle clinical trial with norelgestromin and ethinyl estradiol transdermal system there were no clinically significant changes in fasting blood glucose from baseline to end of treatment.

Consider alternative contraception for women with uncontrolled dyslipidemia. A small proportion of women will have adverse lipid changes while on hormonal contraceptives.

Women with hypertriglyceridemia, or a family history thereof, may be at an increased risk of pancreatitis when using hormonal contraceptives.

5.8 Headache

If a woman taking norelgestromin and ethinyl estradiol transdermal system develops new headaches that are recurrent, persistent or severe, evaluate the cause and discontinue norelgestromin and ethinyl estradiol transdermal system if indicated.

Consider discontinuation of norelgestromin and ethinyl estradiol transdermal system in the case of increased frequency or severity of migraine during hormonal contraceptive use (which may be prodromal of a cerebrovascular event).

5.9 Bleeding Irregularities

Unscheduled Bleeding and Spotting

Unscheduled (breakthrough) bleeding and spotting sometimes occur in women using norelgestromin and ethinyl estradiol transdermal system. Consider non-hormonal causes and take adequate diagnostic measures to rule out malignancy, other pathology, or pregnancy in the event of unscheduled bleeding, as in the case of any abnormal vaginal bleeding. If pathology and pregnancy have been excluded, time or a change to another contraceptive product may resolve the bleeding.

In the clinical trials, most women started their scheduled (withdrawal) bleeding on the fourth day of the drug-free interval, and the median duration of withdrawal bleeding was 5 to 6 days. On average, 26% of women per cycle had 7 or more total days of bleeding and/or spotting (this includes both scheduled and unscheduled bleeding and/or spotting). Three clinical studies of the efficacy of norelgestromin and ethinyl estradiol transdermal system in preventing pregnancy assessed scheduled and unscheduled bleeding [see Clinical Studies (14)] in 3,330 women who completed 22,155 cycles of exposure. A total of 36 (1.1%) of the women discontinued norelgestromin and ethinyl estradiol transdermal system at least in part, due to bleeding or spotting.

Table 2 summarizes the proportion of subjects who experienced unscheduled (breakthrough) bleeding/spotting by treatment cycle.

Table 2: Unscheduled (Breakthrough) Bleeding/Spotting (Subjects Evaluable for Efficacy)

Treatment Cycle | Pooled data from 3 studies N=3319
Treatment Cycle | n | %*
Cycle 1 | 2994 | 18.2
Cycle 2 | 2743 | 11.9
Cycle 3 | 2699 | 11.6
Cycle 4 | 2541 | 10.1
Cycle 5 | 2532 | 9.2
Cycle 6 | 2494 | 8.3
Cycle 7 | 698 | 8.3
Cycle 8 | 692 | 8.7
Cycle 9 | 654 | 8.6
Cycle 10 | 621 | 8.7
Cycle 11 | 631 | 8.9
Cycle 12 | 617 | 6.3
Cycle 13 | 611 | 8.0

*Percentage of subjects with breakthrough bleeding/spotting events.

Amenorrhea and Oligomenorrhea

In the event of amenorrhea, consider the possibility of pregnancy. If the patient has not adhered to the prescribed dosing schedule (missed one patch or started the patch on a day later than she should have), consider the possibility of pregnancy at the time of the first missed period and take appropriate diagnostic measures. If the patient has adhered to the prescribed regimen and misses two consecutive periods, rule out pregnancy.

Some women may encounter amenorrhea or oligomenorrhea after discontinuation of hormonal contraceptive use, especially when such a condition was pre-existent.

5.10 Hormonal Contraceptive Use Before or During Early Pregnancy

Extensive epidemiological studies have revealed no increased risk of birth defects in women who have used oral contraceptives prior to pregnancy. Studies also do not suggest a teratogenic effect, particularly in so far as cardiac anomalies and limb reduction defects are concerned, when oral contraceptives are taken inadvertently during early pregnancy. Discontinue norelgestromin and ethinyl estradiol transdermal system use if pregnancy is confirmed.

Administration of CHCs should not be used as a test for pregnancy [see Use in Specific Populations (8.1)].

5.11 Depression

Carefully observe women with a history of depression and discontinue norelgestromin and ethinyl estradiol transdermal system if depression recurs to a serious degree.

5.12 Malignant Neoplasms

Breast Cancer
Norelgestromin and ethinyl estradiol transdermal system are contraindicated in females who currently have or have had breast cancer because breast cancer may be hormonally sensitive [see Contraindications (4)].
Epidemiology studies have not found a consistent association between use of combined oral contraceptives (COCs) and breast cancer risk. Studies do not show an association between ever (current or past) use of COCs and risk of breast cancer. However, some studies report a small increase in the risk of breast cancer among current or recent users (<6 months since last use) and current users with longer duration of COC use [see Postmarketing Experience (6.2)].
Cervical Cancer
Some studies suggest that COC use has been associated with an increase in the risk of cervical cancer or intraepithelial neoplasia. However, there continues to be controversy about the extent to which such findings may be due to differences in sexual behavior and other factors.

5.13 Effect on Binding Globulins

The estrogen component of CHCs may raise the serum concentrations of thyroxine-binding globulin, sex hormone-binding globulin and cortisol-binding globulin. The dose of replacement thyroid hormone or cortisol therapy may need to be increased.

5.14 Monitoring

A woman who is taking hormonal contraceptive should have routine visits with her healthcare provider for a blood pressure check and for other indicated healthcare.

5.15 Hereditary Angioedema

In women with hereditary angioedema, exogenous estrogens may induce or exacerbate symptoms of angioedema.

5.16 Chloasma

Chloasma may occasionally occur, especially in women with a history of chloasma gravidarum. Women with a tendency to chloasma should avoid exposure to the sun or ultraviolet radiation while using norelgestromin and ethinyl estradiol transdermal system.

6 ADVERSE REACTIONS

The following serious adverse reactions with the use of combination hormonal contraceptives, including norelgestromin and ethinyl estradiol transdermal system, are discussed elsewhere in the labeling:

- Serious cardiovascular events and stroke [see Boxed Warning and Warnings and Precautions (5.1)]
- Vascular events, including venous and arterial thromboembolic events [see Warnings and Precautions (5.1)]
- Liver disease [see Warnings and Precautions (5.3)]

Adverse reactions commonly reported by users of combination hormonal contraceptives are:

- Irregular uterine bleeding
- Nausea
- Breast tenderness
- Headache

6.1 Clinical Trials Experience

Because clinical trials are conducted under widely varying conditions, adverse reaction rates observed in the clinical trials of a drug cannot be directly compared to rates in the clinical trials of another drug and may not reflect the rates observed in clinical practice.

The data described below reflect exposure to norelgestromin and ethinyl estradiol transdermal system in 3330 sexually active women (3322 of whom had safety data) who participated in three Phase 3 clinical trials designed to evaluate contraceptive efficacy and safety. These subjects received six or 13 cycles of contraception (norelgestromin and ethinyl estradiol transdermal system or an oral contraceptive comparator in 2 of the trials). The women ranged in age from 18 to 45 years and were predominantly white (91%).

The most common adverse reactions (≥ 5%) reported during clinical trials were breast symptoms, nausea/vomiting, headache, application site disorder, abdominal pain, dysmenorrhea, vaginal bleeding and menstrual disorders, and mood, affect and anxiety disorders. The most common events leading to discontinuation were application site reaction, breast symptoms (including breast discomfort, engorgement and pain), nausea and/or vomiting, headache and emotional lability.

Adverse drug reactions reported by ≥ 2.5% of norelgestromin and ethinyl estradiol transdermal system-treated subjects in these trials are shown in Table 3.

Table 3: Adverse Drug Reactions Reported by ≥ 2.5% of Norelgestromin and Ethinyl Estradiol Transdermal System-treated Subjects in Three Phase 3 Clinical Trials

System/Organ Class* Adverse reaction | Norelgestromin and Ethinyl Estradiol Transdermal System (n = 3322)
Reproductive system and breast disorders
Breast symptoms† | 22.4%
Dysmenorrhea | 7.8%
Vaginal bleeding and menstrual disorders† | 6.4%
Gastrointestinal disorders
Nausea | 16.6%
Abdominal pain† | 8.1%
Vomiting | 5.1%
Diarrhea | 4.2%
Nervous system disorders
Headache | 21.0%
Dizziness | 3.3%
Migraine | 2.7%
General disorders and administration site conditions
Application site disorder† | 17.1%
Fatigue | 2.6%
Psychiatric disorders
Mood, affect and anxiety disorders† | 6.3%
Skin and subcutaneous tissue disorders
Acne | 2.9%
Pruritus | 2.5%
Infections and infestations
Vaginal yeast infection† | 3.9%
Investigations
Weight increased | 2.7%

*MedDRA version 10.0

†Represents a bundle of similar terms

Additional adverse drug reactions that occurred in < 2.5% of norelgestromin and ethinyl estradiol transdermal system-treated subjects in the above clinical trials datasets are:

- Gastrointestinal disorders : Abdominal distension
- General disorders and administration site conditions : Fluid retention^1, malaise
- Hepatobiliary disorders : Cholecystitis
- Investigations : Blood pressure increased, lipid disorders^1
- Musculoskeletal and connective tissue disorders : Muscle spasms
- Psychiatric disorders : Insomnia, libido decreased, libido increased
- Reproductive system and breast disorders : Galactorrhea, genital discharge, premenstrual syndrome, uterine spasm, vaginal discharge, vulvovaginal dryness
- Respiratory, thoracic and mediastinal disorders : Pulmonary embolism
- Skin and subcutaneous tissue disorders : Chloasma, dermatitis contact, erythema, skin irritation

^1Represents a bundle of similar terms

6.2 Postmarketing Experience

Five studies that compared breast cancer risk between ever-users (current or past use) of COCs and never-users of COCs reported no association between ever use of COCs and breast cancer risk, with effect estimates ranging from 0.90 - 1.12 (Figure 2).

Three studies compared breast cancer risk between current or recent COC users (<6 months since last use) and never users of COCs (Figure 2). One of these studies reported no association between breast cancer risk and COC use. The other two studies found an increased relative risk of 1.19 - 1.33 with current or recent use. Both of these studies found an increased risk of breast cancer with current use of longer duration, with relative risks ranging from 1.03 with less than one year of COC use to approximately 1.4 with more than 8-10 years of COC use.

Figure 2: Risk of Breast Cancer with Combined Oral Contraceptive Use

RR = relative risk; OR = odds ration; HR = hazard ration. "ever COC" are females with current or past COC use; "never COC use" are fmales that never used COCs.

The following adverse reactions (Table 4) have been identified during postapproval use of norelgestromin and ethinyl estradiol transdermal system. Because these reactions are reported voluntarily from a population of uncertain size, it is not always possible to reliably estimate their frequency or establish a causal relationship to drug exposure.

Table 4: Alphabetical List of Adverse Drug Reactions Identified During Postmarketing Experience with Norelgestromin and Ethinyl Estradiol Transdermal System by System Organ Class*

System Organ Class | Adverse Drug Reactions
Cardiac disorders | Myocardial infarction†
Endocrine disorders | Hyperglycemia, insulin resistance
Eye disorders | Contact lens intolerance or complication
Gastrointestinal disorders | Colitis
General disorders and administration site conditions | Application site reaction†, edema†
Hepatobiliary disorders | Blood cholesterol abnormal, cholelithiasis, cholestasis, hepatic lesion, jaundice cholestatic, low density lipoprotein increased
Immune system disorders | Allergic reaction†, urticaria
Investigations | Blood glucose abnormal, blood glucose decreased
Metabolism and nutrition disorders | Increased appetite
Neoplasms benign, malignant and unspecified (Incl. cysts and polyps) | Breast cancer†, cervix carcinoma, hepatic adenoma, hepatic neoplasm
Nervous system disorders | Dysgeusia, migraine with aura
Psychiatric disorders | Anger, emotional disorder, frustration, irritability
Reproductive system and breast disorders | Breast mass, cervical dysplasia, fibroadenoma of breast, menstrual disorder†, suppressed lactation, uterine leiomyoma
Skin and subcutaneous tissues disorders | Alopecia, eczema, erythema multiforme, erythema nodosum, photosensitivity reaction, pruritus generalized, rash†, seborrheic dermatitis, skin reaction
Vascular disorders | Arterial thrombosis†, cerebrovascular accident†, deep vein thrombosis†, hemorrhage intracranial†, hypertension, hypertensive crisis, pulmonary embolism†, thrombosis†

*MedDRA version 10.0

†Represents a bundle of similar terms

7 DRUG INTERACTIONS

Consult the labeling of concurrently-used drugs to obtain further information about interactions with hormonal contraceptives or the potential for enzyme alterations.

7.1 Effects of Other Drugs on Combined Hormonal Contraceptives

Substances Decreasing the Plasma Concentrations of CHCs and Potentially Diminishing the Efficacy of CHCs

Drugs or herbal products that induce certain enzymes, including cytochrome P450 3A4 (CYP3A4), may decrease the plasma concentrations of CHCs and potentially diminish the effectiveness of CHCs or increase breakthrough bleeding. Some drugs or herbal products that may decrease the effectiveness of hormonal contraceptives include phenytoin, barbiturates, carbamazepine, bosentan, felbamate, griseofulvin, oxcarbazepine, rifampicin, topiramate, rifabutin, rufinamide, aprepitant, and products containing St. John's wort. Interactions between hormonal contraceptives and other drugs may lead to breakthrough bleeding and/or contraceptive failure. Counsel women to use an alternative method of contraception or a back-up method when enzyme inducers are used with CHCs, and to continue back-up contraception for 28 days after discontinuing the enzyme inducer to ensure contraceptive reliability.

Substances Increasing the Plasma Concentrations of CHCs

Co-administration of atorvastatin or rosuvastatin and certain CHCs containing EE increase AUC values for EE by approximately 20% to 25%. Ascorbic acid and acetaminophen may increase plasma EE concentrations, possibly by inhibition of conjugation. CYP3A4 inhibitors such as itraconazole, voriconazole, fluconazole, grapefruit juice, or ketoconazole may increase plasma hormone concentrations.

Human Immunodeficiency Virus (HIV)/Hepatitis C Virus (HCV) Protease Inhibitors and Non-Nucleoside Reverse Transcriptase Inhibitors

Significant changes (increase or decrease) in the plasma concentrations of estrogen and/or progestin have been noted in some cases of co-administration with HIV protease inhibitors (decrease [e.g., nelfinavir, ritonavir, darunavir/ritonavir, (fos)amprenavir/ritonavir, lopinavir/ritnoavir, and tipranavir/ritonavir] or increase [e.g., indinavir and atazanavir/ritonavir])/HCV protease inhibitors or with non-nucleoside reverse transcriptase inhibitors (decrease [e.g., nevirapine] or increase [e.g., etravirine]).

7.2 Effects of Combined Hormonal Contraceptives on Other Drugs

CHCs containing EE may inhibit the metabolism of other compounds (e.g., cyclosporine, prednisolone, theophylline, tizanidine, and voriconazole) and increase their plasma concentrations. CHCs have been shown to decrease plasma concentrations of acetaminophen, clofibric acid, morphine, salicylic acid, and temazepam. Significant decrease in plasma concentration of lamotrigine has been shown, likely due to induction of lamotrigine glucuronidation. This may reduce seizure control; therefore, dosage adjustments of lamotrigine may be necessary.

Women on thyroid hormone replacement therapy may need increased doses of thyroid hormone because serum concentration of thyroid-binding globulin increases with use of CHCs [see Warnings and Precautions (5.13)].

7.3 Concomitant Use with HCV Combination Therapy – Liver Enzyme Elevation

Do not co-administer norelgestromin and ethinyl estradiol transdermal system with HCV drug combinations containing ombitasvir/paritaprevir/ritonavir, with or without dasabuvir, due to potential for ALT elevations [see Warnings and Precautions (5.4)].

7.4 Interference with Laboratory Tests

The use of contraceptive steroids may influence the results of certain laboratory tests, such as coagulation factors, lipids, glucose tolerance, and binding proteins.

8 USE IN SPECIFIC POPULATIONS

8.1 Pregnancy

There is little or no increased risk of birth defects in women who inadvertently use hormonal contraceptives during early pregnancy. Epidemiologic studies and meta-analyses have not found an increased risk of genital or non-genital birth defects (including cardiac anomalies and limb reduction defects) following exposure to low dose hormonal contraceptives prior to conception or during early pregnancy.

The administration of hormonal contraceptives to induce withdrawal bleeding should not be used as a test for pregnancy. Hormonal contraceptives should not be used during pregnancy to treat threatened or habitual abortion.

8.3 Nursing Mothers

The effects of norelgestromin and ethinyl estradiol transdermal system in nursing mothers have not been evaluated and are unknown. When possible, advise the nursing mother to use other forms of contraception until she has completely weaned her child. Estrogen-containing CHCs can reduce milk production in breastfeeding mothers. This is less likely to occur once breastfeeding is well-established; however, it can occur at any time in some women. Small amounts of contraceptive steroids and/or metabolites are present in breast milk.

8.4 Pediatric Use

Safety and efficacy of norelgestromin and ethinyl estradiol transdermal system have been established in women of reproductive age. Efficacy is expected to be the same for post-pubertal adolescents under the age of 18 and for users 18 years and older. Use of this product before menarche is not indicated.

8.5 Geriatric Use

Norelgestromin and ethinyl estradiol transdermal system has not been studied in postmenopausal women and is not indicated in this population.

8.6 Hepatic Impairment

No studies with norelgestromin and ethinyl estradiol transdermal system have been conducted in women with hepatic impairment. However, steroid hormones may be poorly metabolized in patients with impaired liver function. Acute or chronic disturbances of liver function may necessitate the discontinuation of combined hormonal contraceptive use until markers of liver function return to normal and combined hormonal contraceptive causation has been excluded. [See Contraindications (4) and Warnings and Precautions (5.3).]

8.7 Renal Impairment

No studies with norelgestromin and ethinyl estradiol transdermal system have been conducted in women with renal impairment.

8.8 BMI and Weight Considerations

Norelgestromin and ethinyl estradiol transdermal system is contraindicated in women with a BMI ≥ 30 kg/m^2 because of the potential increased risk of VTE [see Contraindications (4) and Warnings and Precautions (5.1)].

Norelgestromin and ethinyl estradiol transdermal system may be less effective in preventing pregnancy in women who weigh 198 lbs. or more [see Clinical Studies (14)].

10 OVERDOSAGE

Overdosage may cause nausea and vomiting, and withdrawal bleeding may occur in women. In case of suspected overdose, all norelgestromin and ethinyl estradiol transdermal system patches should be removed and symptomatic treatment given.

11 DESCRIPTION

Norelgestromin and ethinyl estradiol transdermal system is a transdermal system with a contact surface area of 15.75 cm^2. It contains 4.678 mg norelgestromin, USP (NGMN) and 0.53 mg ethinyl estradiol, USP (EE), and its delivery rate is approximately 150 mcg of NGMN and 35 mcg of EE per day. Systemic exposures (as measured by area under the curve [AUC] and steady state concentration [Css]) of NGMN and EE during use of norelgestromin and ethinyl estradiol transdermal system are higher and the Cmax is lower than those produced by an oral contraceptive containing NGM 250 mcg / EE 35 mcg. [See Boxed Warning and Clinical Pharmacology (12.3).]

Norelgestromin and ethinyl estradiol transdermal system is a thin, matrix-type transdermal system consisting of three layers. The backing layer is composed of a peach flexible film consisting of a pigmented polyethylene outer layer and a polyester inner layer. It provides structural support and protects the middle adhesive layer from the environment. The middle layer contains crospovidone, lauryl lactate, polyisobutylene/polybutene adhesive and non-woven polyester fabric as inactive components. The active components in this layer are the hormones, NGMN and EE. The third layer is the release liner, which protects the adhesive layer during storage and is removed just prior to application. It is a transparent polyethylene terephthalate (PET) film with a polydimethylsiloxane coating on the side that is in contact with the middle adhesive layer.

The outside of the backing layer is printed with "Norelgestromin and ethinyl estradiol 150/35 mcg per day" in red ink.

Norelgestromin and ethinyl estradiol transdermal system is packaged with additional piece of protective film above the system within each pouch. This piece of protective film is removed and discarded at the time of use.

The structural formulas of the components are:

Molecular weight, NGMN: 327.47

Molecular weight, EE: 296.41

Chemical name for NGMN: 18, 19-dinorpregn-4-en-20-yn-3-one, 13-ethyl-, 17-hydroxy, 3-oxime, (17α)-

Chemical name for EE: 19-Norpregna-1,3,5(10)-trien-20-yne-3, 17β-diol, (17α)-

12 CLINICAL PHARMACOLOGY

12.1 Mechanism of Action

NGMN is the active progestin largely responsible for the progestational activity that occurs in women following application of norelgestromin and ethinyl estradiol transdermal system. NGMN is also the primary active metabolite produced following oral administration of NGM, the progestin component of some oral contraceptive products.

Combination hormonal contraceptives act by suppression of gonadotropins. Although the primary mechanism of this action is inhibition of ovulation, other alterations include changes in the cervical mucus (which increase the difficulty of sperm entry into the uterus) and the endometrium (which reduce the likelihood of implantation).

12.2 Pharmacodynamics

One clinical trial assessed the return of hypothalamic-pituitary-ovarian axis function post-therapy and found that follicle-stimulating hormone (FSH), luteinizing hormone (LH), and estradiol mean values, though suppressed during therapy, returned to near baseline values during the 6 weeks post-therapy.

12.3 Pharmacokinetics

Absorption

The systemic delivery rate of NGMN and EE from norelgestromin and ethinyl estradiol transdermal system is approximately 150 mcg of NGMN and 35 mcg of EE per day based on a comparative analysis with intravenous (IV) data. Following a single application of norelgestromin and ethinyl estradiol transdermal system, both NGMN and EE reach a plateau by approximately 48 hours. Pooled data from the 3 clinical studies have demonstrated that steady state is reached within 2 weeks of application. In one of the clinical studies, Css concentrations across all subjects ranged from 0.305 to 1.53 ng/mL for NGMN and from 23 to 137 pg/mL for EE.

Absorption of NGMN and EE following application of norelgestromin and ethinyl estradiol transdermal system to the buttock, upper outer arm, abdomen and upper torso (excluding breast) was examined. While absorption from the abdomen was slightly lower than from other sites, absorption from these anatomic sites was considered to be therapeutically equivalent.

The mean (%CV) PK parameters Css and AUC0-168 for NGMN and EE following a single buttock application of norelgestromin and ethinyl estradiol transdermal system are summarized in Table 5.

In multiple dose studies, AUC0-168 for NGMN and EE was found to increase over time (Table 5). In a three-cycle study, these PK parameters reached steady state conditions during Cycle 3 (Figures 3 and 4). Upon removal of the patch, serum levels of EE and NGMN reach very low or non-measurable levels within 3 days.

Table 5: Mean (%CV*) PK Parameters of NGMN and EE Following Three Consecutive Cycles of Norelgestromin and Ethinyl Estradiol Transdermal System Wear on the Buttock

Analyte | Parameter | Cycle 1 Week 1 | Cycle 3 Week 1 | Cycle 3 Week 2 | Cycle 3 Week 3
NGMN | Css(ng/mL) | 0.70 (39.4) | 0.70 (41.8) | 0.80 (28.7) | 0.70 (45.3)
NGMN | AUC0-168(ng·h/mL) | 107 (44.2) | 105 (43.2) | 132 (43.4) | 120 (43.9)
NGMN | t1/2(h) | nc | nc | nc | 32.1 (40.3)
EE | Css(pg/mL) | 46.4 (38.5) | 47.6 (36.4) | 59.0 (42.5) | 49.6 (54.4)
EE | AUC0-168(pg·h/mL) | 6796 (39.3) | 7160 (40.4) | 10054 (41.8) | 8840 (58.6)
EE | t1/2(h) | nc | nc | nc | 21 (43.2)
nc = not calculated *%CV is % of Coefficient of variation = 100 (standard deviation/mean)

Figure 3: Mean Serum NGMN Concentrations (ng/mL) in Healthy Female Volunteers Following Application of Norelgestromin and Ethinyl Estradiol Transdermal System on the Buttock for Three Consecutive Cycles (Vertical arrow indicates time of patch removal)

Figure 4: Mean Serum EE Concentrations (pg/mL) in Healthy Female Volunteers Following Application of Norelgestromin and Ethinyl Estradiol Transdermal System on the Buttock for Three Consecutive Cycles (Vertical arrow indicates time of patch removal.)

The absorption of NGMN and EE following application of norelgestromin and ethinyl estradiol transdermal system was studied under conditions encountered in a health club (sauna, whirlpool and treadmill) and in a cold water bath. The results indicated that for NGMN, there were no significant treatment effects on Css or AUC when compared to normal wear. For EE, increased exposures were observed due to sauna, whirlpool and treadmill. There was no significant effect of cold water on these parameters.

Results from a study of consecutive norelgestromin and ethinyl estradiol transdermal system wear for 7 days and 10 days indicated that serum concentrations of NGMN and EE dropped slightly during the first 6 hours after the patch replacement, and recovered within 12 hours. By Day 10 of patch administration, both NGMN and EE concentrations had decreased by approximately 25% when compared to Day 7 concentrations.

Metabolism

Since NGMN and EE are delivered transdermally, first-pass metabolism (via the gastrointestinal tract and/or liver) of NGMN and EE that would be expected with oral administration does not occur. Hepatic metabolism of NGMN occurs and metabolites include norgestrel, which is highly bound to SHBG, and various hydroxylated and conjugated metabolites. EE is also metabolized to various hydroxylated products and their glucuronide and sulfate conjugates.

Distribution

NGMN and norgestrel (a serum metabolite of NGMN) are highly bound (> 97%) to serum proteins. NGMN is bound to albumin and not to SHBG, while norgestrel is bound primarily to SHBG, which limits its biological activity. EE is extensively bound to serum albumin and induces an increase in the serum concentrations of SHBG (see Table 5).

Elimination

Following removal of patches, the elimination kinetics of NGMN and EE were consistent for all studies with half-life values of approximately 28 hours and 17 hours, respectively. The metabolites of NGMN and EE are eliminated by renal and fecal pathways.

Transdermal versus Oral Contraceptives

The norelgestromin and ethinyl estradiol transdermal system delivers EE and NGMN over a 7-day period while oral contraceptives (containing NGM 250 mcg / EE 35 mcg) are administered on a daily basis. Figures 5 and 6 present mean PK profiles for EE and NGMN following administration of an oral contraceptive (containing NGM 250 mcg / EE 35 mcg) compared to the 7-day norelgestromin and ethinyl estradiol transdermal system (containing NGMN 4.678 mg / EE 0.53 mg) during Cycle 2 in 32 healthy female volunteers.

Figure 5: Mean Serum Concentration-Time Profiles of NGMN Following Once-Daily Administration of an Oral Contraceptive for Two Cycles or Application of Norelgestromin and Ethinyl Estradiol Transdermal System for Two Cycles to the Buttock in Healthy Female Volunteers. [Oral contraceptive: Cycle 2, Days 15 to 21, Norelgestromin and Ethinyl Estradiol Transdermal System: Cycle 2, Week 3]

Figure 6: Mean Serum Concentration-Time Profiles of EE Following Once-Daily Administration of an Oral Contraceptive for Two Cycles or Application of Norelgestromin and Ethinyl Estradiol Transdermal System for Two Cycles to the Buttock in Healthy Female Volunteers. [Oral contraceptive: Cycle 2, Days 15 to 21, Norelgestromin and Ethinyl Estradiol Transdermal System: Cycle 2, Week 3]

Table 6 provides the mean (%CV) for NGMN and EE pharmacokinetic (PK) parameters.

Table 6: Mean (%CV) NGMN and EE Steady State Pharmacokinetic Parameters Following Application of Norelgestromin and Ethinyl Estradiol Transdermal System and Once-Daily Administration of an Oral Contraceptive (containing NGM 250 mcg / EE 35 mcg) in Healthy Female Volunteers

Parameter | Norelgestromin and Ethinyl Estradiol Transdermal System* | ORAL CONTRACEPTIVE†
NGMN‡
Cmax (ng/mL) | 1.12 (33.6) | 2.16 (25.2)
AUC0-168(ng·h/mL) | 145 (36.8) | 123 (30.2)§
Css(ng/mL) | 0.888 (36.6) | 0.732 (30.2)¶
EE
Cmax (pg/mL) | 97.4 (31.6) | 133 (27.7)
AUC0-168(pg·h/mL) | 12,971 (33.1) | 8,281(26.9)§
Css(pg/mL) | 80.0 (33.5) | 49.3 (26.9)¶

*Cycle 2, Week 3

†Cycle 2, Day 21

‡NGM is rapidly metabolized to NGMN following oral administration

§Average weekly exposure, calculated as AUC24 x 7

¶Cavg

In general, overall exposure for NGMN and EE (AUC and Css) was higher in subjects treated with norelgestromin and ethinyl estradiol transdermal system for both Cycle 1 and Cycle 2, compared to that for the oral contraceptive, while Cmax values were higher in subjects administered the oral contraceptive. Under steady state conditions, AUC0-168 and Css for EE were approximately 55% and 60% higher, respectively, for the transdermal patch, and the Cmax was about 35% higher for the oral contraceptive, respectively. Inter-subject variability (%CV) for the PK parameters following delivery from norelgestromin and ethinyl estradiol transdermal system was higher relative to the variability determined from the oral contraceptive. The mean PK profiles are different between the two products and caution should be exercised when making a direct comparison of these PK parameters.

In Table 7, percent change in concentrations (%CV) of markers of systemic estrogenic activity (Sex Hormone Binding Globulin [SHBG] and Corticosteroid Binding Globulin [CBG]) from Cycle 1 Day 1 to Cycle 1 Day 22 is presented. Percent change in SHBG concentrations was higher for norelgestromin and ethinyl estradiol transdermal system users compared to women taking the oral contraceptive; percent change in CBG concentrations was similar for norelgestromin and ethinyl estradiol transdermal system and oral contraceptive users. Within each group, the absolute values for SHBG were similar for Cycle 1, Day 22 and Cycle 2, Day 22.

Table 7: Mean Percent Change (%CV) in SHBG and CBG Concentrations Following Once-Daily Administration of an Oral Contraceptive (containing NGM 250 mcg / EE 35 mcg) for One Cycle and Application of Norelgestromin and Ethinyl Estradiol Transdermal System for One Cycle in Healthy Female Volunteers

Parameter | Norelgestrmin and Ethinyl Estradiol Transdermal System | ORAL CONTRACEPTIVE
 | (% change from Day 1 to Day 22) | (% change from Day 1 to Day 22)
SHBG | 334 (39.3) | 200 (43.2)
CBG | 153 (40.2) | 157 (33.4)

Drug Interactions

In a PK drug interaction study, oral administration of tetracycline HCl, 500 mg four times daily for 3 days prior to and 7 days during wear of norelgestromin and ethinyl estradiol transdermal system did not significantly affect the PK of NGMN or EE.

Use in Specific Populations

Effects of Age, Body Weight, Body Surface Area and Race

The effects of age, body weight, body surface area and race on the PK of NGMN and EE were evaluated in 230 healthy women from nine pharmacokinetic studies of single 7-day applications of norelgestromin and ethinyl estradiol transdermal system. For both NGMN and EE, increasing age, body weight and body surface area each were associated with slight decreases in Css and AUC values. However, only a small fraction (10% to 25%) of the overall variability in the PK of NGMN and EE following application of norelgestromin and ethinyl estradiol transdermal system may be associated with any or all of the above demographic parameters. There was no significant effect of race with respect to Caucasians, Hispanics and Blacks.

13 NONCLINICAL TOXICOLOGY

13.1 Carcinogenesis, Mutagenesis, Impairment of Fertility

See Warnings and Precautions (5.3, 5.12)and Use in Specific Populations (8.1).

Norelgestromin was tested in in vitro mutagenicity assays (bacterial plate incorporation mutation assay, CHO/HGPRT mutation assay, chromosomal aberration assay using cultured human peripheral lymphocytes) and in one in vivo test (rat micronucleus assay) and found to have no genotoxic potential.

14 CLINICAL STUDIES

In 3 large clinical trials lasting 12 months, in North America, Europe and South Africa, 3,330 women (ages 18 to 45) completed 22,155 cycles of norelgestromin and ethinyl estradiol transdermal system use, the pregnancy rate in women aged 18 to 35 years was 1.07 (95% confidence interval 0.60, 1.76) per 100 woman-years of norelgestromin and ethinyl estradiol transdermal system use. The racial distribution was 91% Caucasian, 4.9% Black, 1.6% Asian, and 2.4% Other.

With respect to weight, 5 of the 15 pregnancies reported with norelgestromin and ethinyl estradiol transdermal system use were among women with a baseline body weight ≥ 198 lbs., which constituted < 3% of the study population. The greater proportion of pregnancies among women at or above 198 lbs. was statistically significant and suggests that norelgestromin and ethinyl estradiol transdermal system may be less effective in these women.

Patch Adhesion

In the clinical trials with norelgestromin and ethinyl estradiol transdermal system, approximately 2% of the cumulative number of patches completely detached and 3% partially detached. The proportion of subjects with at least one patch that completely detached ranged from 2% to 6%, with a reduction from Cycle 1 (6%) to Cycle 13 (2%). For instructions on how to manage detachment of patches, refer to Dosage and Administration (2).

16 HOW SUPPLIED/STORAGE AND HANDLING

16.1 How Supplied

Norelgestromin and ethinyl estradiol transdermal system is available in one strength of 150 mcg/day NGMN and 35 mcg/day EE.

Norelgestromin and ethinyl estradiol transdermal system is a 15.75 cm^2tan, transdermal system printed with "Norelgestromin and ethinyl estradiol 150/35 mcg per day" in red ink. Each system contains 4.678 mg norelgestromin, USP and 0.53 mg ethinyl estradiol, USP.

Each transdermal system is packaged in a protective pouch.

Norelgestromin and ethinyl estradiol transdermal system is available in cartons (NDC 70710-1190-3); each contains 3 systems.

16.2 Special Precautions for Storage and Disposal

Store at 20° to 25°C (68° to 77°F). [See USP Controlled Room Temperature.]

Store patches in their protective pouches. Apply immediately upon removal from the protective pouch.

Do not store in the refrigerator or freezer.

Used patches still contain some active hormones. The sticky sides of the patch should be folded together and the folded patch placed in a sturdy container, preferably with a child-resistant cap, and the container thrown in the trash. Used patches should not be flushed down the toilet.

17 PATIENT COUNSELING INFORMATION

See FDA-approved patient labeling (Patient Information and Instructions for Use)

17.1 General

Counsel patients about the following information:

- Cigarette smoking increases the risk of serious cardiovascular events from combined hormonal contraceptive use, and that women who are over 35 years old and smoke should not use combined hormonal contraceptives.
- The use of CHCs increases the risk of VTE. However, pregnancy increases the risk of VTE as much or more than the use of CHCs. The risk of VTE in women using CHCs is 3 to 12 cases per 10,000 woman-years. The risk of VTE is highest during the first year of use of CHCs and when restarting hormonal contraception after a break of 4 weeks or longer. The risk of thromboembolic disease due to CHCs gradually disappears after use is discontinued.
- Norelgestromin and ethinyl estradiol transdermal system does not protect against HIV infection (AIDS) and other sexually transmitted infections.
- The Warnings and Precautions associated with combined hormonal contraceptives.
- Norelgestromin and ethinyl estradiol transdermal system is not to be used during pregnancy; if pregnancy occurs during use of norelgestromin and ethinyl estradiol transdermal system, instruct the patient to stop further use.
- Apply a single patch the same day every week (Weeks 1 through 3). Instruct patients what to do in the event a patch is missed. See "WHAT IF I FORGET TO CHANGE MY PATCH?" section in FDA-Approved Patient Labeling.
- Use a back-up or alternative method of contraception when enzyme inducers are used with norelgestromin and ethinyl estradiol transdermal system.
- Combined hormonal contraceptives may reduce breast milk production; this is less likely to occur if breastfeeding is well established.
- Women who start combined hormonal contraceptives postpartum, and who have not yet had a period, should use an additional method of contraception until they have used a patch for 7 consecutive days.
- Amenorrhea may occur. Consider pregnancy in the event of amenorrhea. Rule out pregnancy in the event of amenorrhea in two or more consecutive cycles, amenorrhea in one cycle if the woman has not adhered to the dosing schedule, or if associated with symptoms of pregnancy, such as morning sickness or unusual breast tenderness.
- If the norelgestromin and ethinyl estradiol transdermal system patch becomes partially or completely detached and remains detached, insufficient drug delivery occurs.

○ A patch should not be re-applied if it is no longer sticky, becomes stuck to itself or another surface, has other material stuck to it, or has become loose or fallen off before. If a patch cannot be re-applied, a new patch should be applied immediately. Supplemental adhesives or wraps should not be used.

○ A woman may not be protected from pregnancy if a patch is partially or completely detached for ≥ 24 hours (or if the woman is not sure how long the patch has been detached). She should start a new cycle immediately by applying a new patch. Back-up contraception, such as a condom and spermicide or diaphragm and spermicide, must be used for the first week of the new cycle.

The brands listed are trademarks of their respective owners.

Manufactured by:

Zydus Lifesciences Ltd.

Ahmedabad, India

Distributed by:

Zydus Pharmaceuticals (USA) Inc.

Pennington, NJ 08534

Rev.: 06/23

PATIENT INFORMATION

Norelgestromin and Ethinyl Estradiol Transdermal System
[nor″ el jes′ troe min and eth′ i nil es″ tra dye′ ol]

What is the most important information I should know about norelgestromin and ethinyl estradiol transdermal system?
Do not use norelgestromin and ethinyl estradiol transdermal system if you smoke cigarettes and are over 35 years old. Smoking increases your risk of serious cardiovascular side effects from hormonal birth control methods, including death from heart attack, blood clots or stroke. This risk increases with age and the number of cigarettes you smoke.
Do not use norelgestromin and ethinyl estradiol transdermal system if you have an increased risk for blood clots.
Do not use norelgestromin and ethinyl estradiol transdermal system if your Body Mass Index (BMI) is 30 kg/m^2 or more. Women with a BMI of 30 kg/m^2 or more who use norelgestromin and ethinyl estradiol transdermal system may be at a higher risk for developing blood clots compared to women with a BMI lower than 30 kg/m^2.
Hormonal birth control methods help to lower the chances of becoming pregnant. They do not protect against HIV infection (AIDS) and other sexually transmitted infections.

What is norelgestromin and ethinyl estradiol transdermal system?
Norelgestromin and ethinyl estradiol transdermal system is a birth control patch for women with a BMI less than 30 kg/m^2. It contains two female hormones, an estrogen called ethinyl estradiol, and a progestin called norelgestromin.
Hormones from norelgestromin and ethinyl estradiol transdermal system get into the blood stream and are processed by the body differently than hormones from birth control pills. You will be exposed to about 60% more estrogen if you use norelgestromin and ethinyl estradiol transdermal system than if you use a typical birth control pill containing 35 micrograms of estrogen. In general, increased estrogen may increase the risk of side effects.

How well does norelgestromin and ethinyl estradiol transdermal system work?
Your chance of getting pregnant depends on how well you follow the directions for using norelgestromin and ethinyl estradiol transdermal system. The better you follow the directions, the less chance you have of getting pregnant.
In clinical studies, 1 to 2 out of 100 women got pregnant during the first year that they used the norelgestromin and ethinyl estradiol transdermal system.
Norelgestromin and ethinyl estradiol transdermal system may not be as effective in women weighing more than 198 lbs. (90 kg). If you weigh more than 198 lbs. (90 kg), talk to your healthcare provider about which method of birth control is right for you.
The following chart shows the chance of getting pregnant for women who use different methods of birth control. Each box on the chart contains a list of birth control methods that are similar in effectiveness. The most effective methods are at the top of the chart. The box on the bottom of the chart shows the chance of getting pregnant for women who do not use birth control and are trying to get pregnant.

Do not use norelgestromin and ethinyl estradiol transdermal system if you:
● smoke and are over 35 years old
● have or have had blood clots in your arms, legs, eyes or lungs
● have an inherited problem that makes your blood clot more than normal
● have had a stroke
● have had a heart attack
● have certain heart valve problems or heart rhythm problems that can cause blood clots to form in the heart
● have high blood pressure that medicine cannot control
● have diabetes with kidney, eye, nerve, or blood vessel damage
● have had certain kinds of severe migraine headaches with aura, numbness, weakness or changes in vision, or have any migraine headaches if you are over age 35
● have a BMI of 30 or more
● have liver disease, including liver tumors, take any Hepatitis C drug combination containing ombitasvir/paritaprevir/ritonavir, with or without dasabuvir. This may increase levels of the liver enzyme "alanine aminotransferase" (ALT) in the blood.
● have unexplained vaginal bleeding
● are pregnant or think you may be pregnant. However, norelgestromin and ethinyl estradiol transdermal system is not known to cause birth defects when used by accident during pregnancy.
● have had breast cancer or any cancer that is sensitive to female hormones
Hormonal birth control methods may not be a good choice for you if you have ever had jaundice (yellowing of the skin or eyes) caused by pregnancy or related to previous use of hormonal birth control.
Tell your healthcare provider if you have ever had any of the above conditions. Your healthcare provider may recommend another method of birth control.

Before you use norelgestromin and ethinyl estradiol transdermal system tell your healthcare provider:
● about all your medical conditions
● if you are pregnant or think you are pregnant
● if you are scheduled for surgery. Norelgestromin and ethinyl estradiol transdermal system may increase your risk of blood clots after surgery. You should stop using your norelgestromin and ethinyl estradiol transdermal system patch at least 4 weeks before you have surgery and not restart it until at least 2 weeks after your surgery.
● if you are scheduled for any laboratory tests. Certain blood tests may be affected by hormonal birth control methods.
● are breastfeeding or plan to breastfeed. Hormonal birth control methods that contain estrogen, like norelgestromin and ethinyl estradiol transdermal system, may decrease the amount of milk you make. A small amount of hormones from the norelgestromin and ethinyl estradiol transdermal system patch may pass into your breast milk. Consider another method of birth control until you are ready to stop breastfeeding.
Tell your healthcare provider about all medicines and herbal products that you take.
Some medicines and herbal products may make hormonal birth control less effective, including, but not limited to:
● certain seizure medicines (carbamazepine, felbamate, oxcarbazepine, phenytoin, rufinamide, and topiramate)
● aprepitant
● barbiturates
● bosentan
● griseofulvin
● certain combinations of HIV medicines (nelfinavir, ritonavir, ritonavir-boosted protease inhibitors)
● certain non-nucleoside reverse transcriptase inhibitors (nevirapine)
● rifampin and rifabutin
● St. John's wort
Use another birth control method (such as a condom and spermicide or diaphragm and spermicide) when you take medicines that may make the norelgestromin and ethinyl estradiol transdermal system patch less effective.
Some medicines and grapefruit juice may increase your level of the hormone ethinyl estradiol if used together, including:
● acetaminophen
● ascorbic acid
● medicines that affect how your liver breaks down other medicines (itraconazole, ketoconazole, voriconazole, and fluconazole)
● certain HIV medicines (atazanavir, indinavir)
● atorvastatin
● rosuvastatin
● etravirine
Hormonal birth control methods may interact with lamotrigine, an anti-seizure medicine used for epilepsy. This may increase the risk of seizures, so your healthcare provider may need to adjust the dose of lamotrigine.
Women on thyroid replacement therapy may need increased doses of thyroid hormone.
Know the medicines you take. Keep a list of them to show your doctor and pharmacist when you get a new medicine.

How should I use norelgestromin and ethinyl estradiol transdermal system?
● For detailed instructions, see the step-by-step instructions for using norelgestromin and ethinyl estradiol transdermal system at the end of this Patient Information.
● Use norelgestromin and ethinyl estradiol transdermal system exactly as your healthcare provider tells you to use it.
● Wear 1 norelgestromin and ethinyl estradiol transdermal system patch at a time. Make sure you remove your old norelgestromin and ethinyl estradiol transdermal system patch before applying your new norelgestromin and ethinyl estradiol transdermal system patch.
● Do not skip using any norelgestromin and ethinyl estradiol transdermal system patches, even if you do not have sex often.
● Norelgestromin and ethinyl estradiol transdermal system is applied in a 4-week cycle.
○ Apply your norelgestromin and ethinyl estradiol transdermal system patch 1 time each week for 3 weeks (21 total days).
○ Apply each new norelgestromin and ethinyl estradiol transdermal system patch on the same day of the week. This day will be your "Patch Change Day." For example, if you apply your first norelgestromin and ethinyl estradiol transdermal system patch on a Monday, all of your norelgestromin and ethinyl estradiol transdermal system patches should be applied on a Monday.
○ Do not apply your norelgestromin and ethinyl estradiol transdermal system patch during Week 4. Make sure you remove your old norelgestromin and ethinyl estradiol transdermal system patch. This is your patch-free week. Your menstrual period should start during your patch-free week.
○ Begin a new 4 week cycle by applying a new norelgestromin and ethinyl estradiol transdermal system patch on the day after Week 4 ends. Repeat the cycle of 3 weekly applications followed by a patch-free week.
● Your norelgestromin and ethinyl estradiol transdermal system patch should never be off for more than 7 days in a row. If your norelgestromin and ethinyl estradiol transdermal system patch is off for more than 7 days in a row and you have sex during this time, you could become pregnant.
● If you miss a period you might be pregnant. Some women miss their periods or have light periods on hormonal birth control methods even when they are not pregnant. Call your healthcare provider if you miss 1 period and have not used your norelgestromin and ethinyl estradiol transdermal system patch every day or you miss 2 periods in a row.

What are the possible side effects of norelgestromin and ethinyl estradiol transdermal system?
See "What is the most important information I should know about norelgestromin and ethinyl estradiol transdermal system?"
Norelgestromin and ethinyl estradiol transdermal system may cause serious side effects, including:
● blood clots . Like pregnancy, hormonal birth control methods increase the risk of serious blood clots (see following graph), especially in women who have other risk factors such as smoking, high blood pressure, high levels of fat in the blood, diabetes, obesity, a family history of blood clots, or age greater than 35. This increased risk is highest when you first start using hormonal birth control and when you restart the same or different hormonal birth control after not using it for a month or more. Some studies have reported that women who use norelgestromin and ethinyl estradiol transdermal system have a higher risk of getting a blood clot. Talk with your healthcare provider about your risk of getting a blood clot before using norelgestromin and ethinyl estradiol transdermal system or deciding which type of birth control is right for you.
It is possible to die or be permanently disabled from a problem caused by a blood clot, such as a heart attack or a stroke . Some examples of serious blood clots are blood clots in the:
● legs (deep vein thrombosis)
● lungs (pulmonary embolus)
● eyes (loss of eyesight)
● heart (heart attack)
● brain (stroke)
To put the risk of developing a blood clot into perspective: If 10,000 women who are not pregnant and do not use hormonal birth control are followed for one year, between 1 and 5 of these women will develop a blood clot. The figure below shows the likelihood of developing a serious blood clot for women who are not pregnant and do not use hormonal birth control, for women who use hormonal birth control, for pregnant women, and for women in the first 12 weeks after delivering a baby.
Likelihood of Developing a Serious Blood Clot (Venous Thromboembolism [VTE])
Call your healthcare provider right away if you have:
● leg pain that will not go away
● sudden shortness of breath
● sudden blindness, partial or complete
● severe pain or pressure in your chest
● sudden, severe headache unlike your usual headaches
● weakness or numbness in an arm or leg, or trouble speaking
● yellowing of the skin or eyeballs
Other serious risks include
● liver problems including liver tumors
● gallbladder disease
● high blood pressure
The most common side effects of norelgestromin and ethinyl estradiol transdermal system are:
● breast symptoms (discomfort, swelling, or pain)
● nausea
● headache
● skin irritation, redness, pain, swelling, itching or rash at the patch application site
● stomach pain
● pain during menstruation
● vaginal bleeding and menstrual disorders, such as spotting or bleeding between periods
● mood, affect and anxiety disorders
Some women have spotting or light bleeding, breast tenderness, or feel sick to their stomach during norelgestromin and ethinyl estradiol transdermal system use. If these symptoms occur, do not stop using the norelgestromin and ethinyl estradiol transdermal system patch. The problem will usually go away. If it does not go away, check with your healthcare provider.
Less common side effects are:
● acne
● less sexual desire
● bloating or fluid retention
● blotchy darkening of your skin, especially your face
● high blood sugar, especially in women with diabetes
● high fat (cholesterol, triglycerides) levels in the blood
● depression, especially if you have had depression in the past. Call your healthcare provider immediately if you have any thoughts of harming yourself.
● problems tolerating contact lenses
● weight gain
Tell your healthcare provider about any side effect that bothers you or that does not go away.
These are not all the possible side effects of norelgestromin and ethinyl estradiol transdermal system. For more information, ask your healthcare provider or pharmacist.
Call your healthcare provider for medical advice about side effects. You may report side effects to FDA at 1-800-FDA-1088.

How should I store and throw away used norelgestromin and ethinyl estradiol transdermal system patches?
● Store at room temperature between 20°C to 25°C (68°F to 77°F).
● Do not store norelgestromin and ethinyl estradiol transdermal system patches outside of their pouches. Apply immediately upon removal from the protective pouch.
● Do not store in the refrigerator or freezer.
● Used norelgestromin and ethinyl estradiol transdermal system patches still contain some active hormones. To throw away the norelgestromin and ethinyl estradiol transdermal system patch, fold the sticky side of the patch together, place it in a sturdy child-proof container, and place this container in the trash. Do not flush used norelgestromin and ethinyl estradiol transdermal system patches down the toilet.
● Return unused, unneeded, or expired patches to your pharmacist.
Keep norelgestromin and ethinyl estradiol transdermal system and all medicines out of the reach of children.

General information about the safe and effective use of norelgestromin and ethinyl estradiol transdermal system.
Medicines are sometimes prescribed for purposes other than those listed in Patient Information. Do not use norelgestromin and ethinyl estradiol transdermal system for a condition for which it was not prescribed. Do not give norelgestromin and ethinyl estradiol transdermal system to other people, even if they have the same symptoms that you have. It may harm them. You can ask your pharmacist or healthcare provider for information about norelgestromin and ethinyl estradiol transdermal system that is written for health professionals.
For more information, contact Zydus Pharmaceuticals (USA) Inc . at 1-877-993-8779 .

What are the ingredients in norelgestromin and ethinyl estradiol transdermal system?
Active ingredient : norelgestromin and ethinyl estradiol
Inactive ingredient : polyethylene, polyester, crospovidone, lauryl lactate, polyisobutylene/polybutene adhesive, non-woven polyester fabric, polyethylene terephthalate (PET) film, and polydimethylsiloxane coating.

Does hormonal birth control cause cancer?
It is not known if hormonal birth control causes breast cancer. Some studies, but not all, suggest that there could be a slight increase in the risk of breast cancer among current users with longer duration of use.
If you have breast cancer now, or have had it in the past, do not use hormonal birth control because some breast cancers are sensitive to hormones.
Women who use hormonal birth control methods maybe have a slightly increased chance of getting cervical cancer. However, this may be due to other reasons such as having more sexual partners.
What should I know about my period when using norelgestromin and ethinyl estradiol transdermal system?
When you use norelgestromin and ethinyl estradiol transdermal system you may have bleeding and spotting between periods, called unplanned bleeding. Unplanned bleeding may vary from slight staining between menstrual periods to breakthrough bleeding which is a flow much like a regular period. Unplanned bleeding occurs most often during the first few months of norelgestromin and ethinyl estradiol transdermal system use, but may also occur after you have been using the patch for some time. Such bleeding may be temporary and usually does not indicate any serious problems. It is important to continue using the patch on schedule. If the unplanned bleeding or spotting is heavy or lasts for more than a few days, you should discuss this with your healthcare provider.
What if I miss my scheduled period when using norelgestromin and ethinyl estradiol transdermal system?
Some women miss periods on hormonal birth control, even when they are not pregnant. However, if you go 2 or more months in a row without a period, or you miss your period after a month where you did not use all of your patches correctly, or you have symptoms associated with pregnancy, such as morning sickness or unusual breast tenderness, call your healthcare provider because you may be pregnant. Stop taking norelgestromin and ethinyl estradiol transdermal system if you are pregnant.
What if I want to become pregnant?
You may stop using norelgestromin and ethinyl estradiol transdermal system whenever you wish. Consider a visit with your healthcare provider for a pre-pregnancy checkup before you stop using the patch.

Manufactured by:
Zydus Lifesciences Ltd.
Ahmedabad, India
Distributed by:
Zydus Pharmaceuticals (USA) Inc.
Pennington, NJ 08534

Rev.: 06/23

Instructions for Use

Norelgestromin and Ethinyl Estradiol Transdermal System

[nor″ el jes′ troe min and eth′ i nil es″ tra dye′ ol]

Norelgestromin and ethinyl estradiol transdermal system is for skin use only.

Do not cut, damage, or alter the norelgestromin and ethinyl estradiol transdermal system patch in any way.

How to start using your norelgestromin and ethinyl estradiol transdermal system patch:

● If you are not currently using hormonal birth control, you have 2 ways to begin using your norelgestromin and ethinyl estradiol transdermal system patch. Choose the way that is best for you:

○ First day start: Apply your first norelgestromin and ethinyl estradiol transdermal system patch during the first 24 hours of your menstrual period.

○ Sunday start: Apply your first norelgestromin and ethinyl estradiol transdermal system patch on the first Sunday after your menstrual period begins. Use a non-hormonal contraceptive method of birth control, such as a condom and spermicide or diaphragm and spermicide, for the first 7 days of your first cycle only. If your period starts on Sunday, apply your first norelgestromin and ethinyl estradiol transdermal system patch that day, and no back-up birth control is needed.

● If you are changing from oral hormone birth control pills, a vaginal contraceptive ring or another contraceptive transdermal patch to the norelgestromin and ethinyl estradiol transdermal system:

○ Complete your current oral hormone birth control pill cycle, vaginal ring cycle or contraceptive transdermal patch cycle. Apply your first norelgestromin and ethinyl estradiol transdermal system patch on the day you would normally start your next oral birth control pill, patch or insert your next vaginal ring.

○ If you do not get your period within 1 week after taking your last active pill, removing your last vaginal ring or contraceptive transdermal patch, check with your healthcare provider to make sure you are not pregnant. You may still go ahead and start norelgestromin and ethinyl estradiol transdermal system for contraception.

○ If you apply your norelgestromin and ethinyl estradiol transdermal system patch more than 1 week after taking your last active oral hormone birth control pill, removing your last vaginal ring or contraceptive transdermal patch, use a non-hormonal contraceptive method, such as a condom and spermicide or diaphragm and spermicide, with the norelgestromin and ethinyl estradiol transdermal system patch for the first 7 days of patch use.

● If you are starting norelgestromin and ethinyl estradiol transdermal system after childbirth:

○ If you are not breastfeeding, wait 4 weeks before using norelgestromin and ethinyl estradiol transdermal system and use a non-hormonal contraceptive method of birth control, such as a condom and spermicide or diaphragm and spermicide, for the first 7 days of your first cycle only. If you have had sex since your baby was born, wait for your first period, or see your healthcare provider to make sure you are not pregnant before starting norelgestromin and ethinyl estradiol transdermal system.

● If you are starting norelgestromin and ethinyl estradiol transdermal system after a miscarriage or abortion:

○ You may start norelgestromin and ethinyl estradiol transdermal system immediately after a miscarriage or abortion that occurs in the first 12 weeks (first trimester) of pregnancy. You do not need to use another contraceptive method.

○ If you do not start norelgestromin and ethinyl estradiol transdermal system within 5 days after a first trimester miscarriage or abortion, use a non-hormonal contraceptive method of birth control, such as a condom and spermicide or diaphragm and spermicide, while you wait for your period to start. You have 2 ways to begin using your norelgestromin and ethinyl estradiol transdermal system patch. Choose the way that is best for you:

▪ First day start: Apply your first norelgestromin and ethinyl estradiol transdermal system patch during the first 24 hours of your menstrual period.

▪ Sunday start: Apply your first norelgestromin and ethinyl estradiol transdermal system patch on the first Sunday after your menstrual period begins. Use a non-hormonal contraceptive method of birth control, such as a condom and spermicide or diaphragm and spermicide, for the first 7 days of your first cycle only. If your period starts on Sunday, apply your first norelgestromin and ethinyl estradiol transdermal system patch that day, and no back-up birth control is needed.

○ If you are starting norelgestromin and ethinyl estradiol transdermal system after a miscarriage or abortion that occurs after the first 12 weeks of pregnancy (second trimester), wait 4 weeks before using norelgestromin and ethinyl estradiol transdermal system and use a non-hormonal contraceptive method of birth control, such as a condom and spermicide or diaphragm and spermicide, for the first 7 days of your first cycle only. If you have had sex since your miscarriage or abortion, wait for your first period, or see your healthcare provider to make sure you are not pregnant before starting norelgestromin and ethinyl estradiol transdermal system.

Figure B is a picture of the norelgestromin and ethinyl estradiol transdermal system patch.

Step 1. Choose a place on your body for your norelgestromin and ethinyl estradiol transdermal system patch

• The norelgestromin and ethinyl estradiol transdermal system patch may be placed on your upper outer arm, abdomen, buttock or back in a place where it will not be rubbed by tight clothing. Avoid the waistline because clothing and belts may cause your patch to be rubbed off.

• Do not apply the patch to your breasts.

• Apply the norelgestromin and ethinyl estradiol transdermal system patch only to skin that is clean, dry, and free of any powder, make-up, cream, oil, or lotion.

• Do not apply the norelgestromin and ethinyl estradiol transdermal system patch to cut or irritated skin, or in the same location as the previous norelgestromin and ethinyl estradiol transdermal system patch.

Step 2: Apply your norelgestromin and ethinyl estradiol transdermal system patch

● Tear open the pouch at the edge. Gently remove the contents of the foil pouch and discard the additional piece of film above the norelgestromin and ethinyl estradiol transdermal system patch.

● Peel away half of the clear plastic. Avoid touching the sticky surface with your fingers.

● Apply the sticky side of the norelgestromin and ethinyl estradiol transdermal system patch to clean, dry skin. Remove the other half of the clear plastic and apply the entire patch to your skin.

● Press firmly on the norelgestromin and ethinyl estradiol transdermal system patch with the palm of your hand for 10 seconds, making sure that the whole patch sticks to your skin.
● Run your fingers over the entire surface area to smooth out any "wrinkles" around the outer edges of the norelgestromin and ethinyl estradiol transdermal system patch.
● Check your norelgestromin and ethinyl estradiol transdermal system patch every day to make sure all edges are sticking correctly.

Step 3: Throwing away your norelgestromin and ethinyl estradiol transdermal system patch

● To throw away the norelgestromin and ethinyl estradiol transdermal system patch, fold the sticky side of the patch together, place it in a sturdy child-proof container, and place the container in the trash.

● Used norelgestromin and ethinyl estradiol transdermal system patches should not be flushed in the toilet.

Important notes:

● Your norelgestromin and ethinyl estradiol transdermal system patch must stick securely to your skin to work properly.

○ Do not try to reapply a norelgestromin and ethinyl estradiol transdermal system patch if it is no longer sticky, if it has become stuck to itself or another surface, or if it has other material stuck to it. Do not tape or wrap the patch to your skin or reapply a patch that is partially adhered to clothing.

● If your norelgestromin and ethinyl estradiol transdermal system patch edge lifts up:

○ Press down firmly on the patch with the palm of your hand for 10 seconds, making sure that the whole patch sticks to your skin. Run your fingers over the entire surface area to smooth out any "wrinkles" around the edges of the norelgestromin and ethinyl estradiol transdermal system patch.

○ If your norelgestromin and ethinyl estradiol transdermal system patch does not stick completely, remove it and apply a new norelgestromin and ethinyl estradiol transdermal system patch.

○ Do not tape or wrap the norelgestromin and ethinyl estradiol transdermal system patch to your skin or reapply a norelgestromin and ethinyl estradiol transdermal system patch that is partially stuck to clothing.

● If your norelgestromin and ethinyl estradiol transdermal system patch has been off or partially off:

○ For less than 1 Day, try to reapply it. If the norelgestromin and ethinyl estradiol transdermal system patch does not stick completely, apply a new norelgestromin and ethinyl estradiol transdermal system patch immediately. No back-up contraception is needed and your "Patch Change Day" will stay the same.

○ For more than 1 Day or if you are not sure for how long, you could become pregnant. To reduce this chance, apply a new norelgestromin and ethinyl estradiol transdermal system patch and start a new 4 week cycle. You will now have a new "Patch Change Day." Use a non-hormonal back-up contraception method such as a condom and spermicide or diaphragm and spermicide for the first week of your new 4 week norelgestromin and ethinyl estradiol transdermal system cycle.

● If you want to move your "Patch Change Day" to a different day of the week, finish your current cycle. Remove your third norelgestromin and ethinyl estradiol transdermal system patch on the correct day.

○ During week 4, the "Patch Free Week" (Day 22 through Day 28), you may choose an earlier "Patch Change Day" by applying a new patch on the day you prefer. You now have a new Day 1 and a new "Patch Change Day."

● If your norelgestromin and ethinyl estradiol transdermal system patch becomes uncomfortable or your application site is red, painful or swollen, change your norelgestromin and ethinyl estradiol transdermal system patch. Remove your norelgestromin and ethinyl estradiol transdermal system patch and apply a new patch to a new location until your next "Patch Change Day."

● If you forget to change or remove your norelgestromin and ethinyl estradiol transdermal system patch:

○ At the start of any patch cycle (Week 1, Day 1):

▪ You could become pregnant. You must use a back-up contraception method for 7 days. Apply the first norelgestromin and ethinyl estradiol transdermal system patch of your new cycle as soon as you remember. You now have a new "Patch Change Day" and a new Day 1.

○ In the middle of your patch cycle (Week 2 or Week 3):

▪ If you forget to change your norelgestromin and ethinyl estradiol transdermal system patch for 1 or 2 days, apply a new norelgestromin and ethinyl estradiol transdermal system patch as soon as you remember. Apply your next patch on your normal "Patch Change Day." No back-up contraception method is needed.

▪ If you forget to change your norelgestromin and ethinyl estradiol transdermal system patch for more than 2 days, you could become pregnant. Start a new 4 week cycle as soon as you remember by putting on a new norelgestromin and ethinyl estradiol transdermal system patch. You now have a different "Patch Change Day" and a new Day 1. You must use a back-up contraception method for the first 7 days of your new cycle.

○ At the end of your patch cycle (Week 4):

▪ If you forget to remove your norelgestromin and ethinyl estradiol transdermal system patch, take it off as soon as you remember. Start your next cycle on your normal "Patch Change Day," the day after Day 28. No back-up contraception method is needed.

● If you forget to apply your norelgestromin and ethinyl estradiol transdermal system patch at the start of your next patch cycle, you could become pregnant. Apply the first norelgestromin and ethinyl estradiol transdermal system patch of your new cycle as soon as you remember. You now have a new "Patch Change Day" and a new Day 1. Use a non-hormonal back-up contraception method such as a condom and spermicide or diaphragm and spermicide for the first 7 days of your new 4 week norelgestromin and ethinyl estradiol transdermal system cycle.

● If you have trouble remembering to change your norelgestromin and ethinyl estradiol transdermal system patch, talk to your healthcare provider about how to make patch changing easier or about using another method of contraception.

● If you are not sure how to use your norelgestromin and ethinyl estradiol transdermal system patch:

○ Use a back-up contraception method such as a condom and spermicide or diaphragm and spermicide anytime you have sex. Make sure to have one of these non-hormonal contraception methods ready at all times.

○ Talk to your healthcare provider for instructions on using your norelgestromin and ethinyl estradiol transdermal system patch.

This Patient Information and Instructions for Use have been approved by the U.S. Food and Drug Administration.

Manufactured by:

Zydus Lifesciences Ltd.

Ahmedabad, India

Distributed by:

Zydus Pharmaceuticals (USA) Inc.

Pennington, NJ 08534

Rev.: 06/23

PRINCIPAL DISPLAY PANEL

NDC 70710-1190-3

Norelgestromin and Ethinyl Estradiol Transdermal System 150/35 mcg per day

This product is intended to prevent pregnancy. It does not protect against HIV infection (AIDS) and other sexually transmitted diseases.

For Transdermal Use Only

Contents: 3 Transdermal Systems

Rx only

Each 15.75 cm^2 system contains 4.678 mg norelgestromin, USP and 0.53 mg ethinyl estradiol, USP. The inactive components are polyisobutylene/polybutene adhesive, crospovidone, lauryl lactate, non-woven polyester fabric, polyester backing film laminate and polyester release liner.

See patient instructions. Apply immediately upon removal from pouch. Each transdermal system is intended to be worn 7 days as prescribed.

Package not child-resistant. Keep out of reach of children.

Do not store unpouched. Store at 20° to 25°C (68° to 77°F). [See USP Controlled Room Temperature.]

Manufactured by:

Zydus Lifesciences Ltd.

Ahmedabad, India

Distributed by:

Zydus Pharmaceuticals (USA) Inc.

Pennington, NJ 08534

Rev.: 10/22